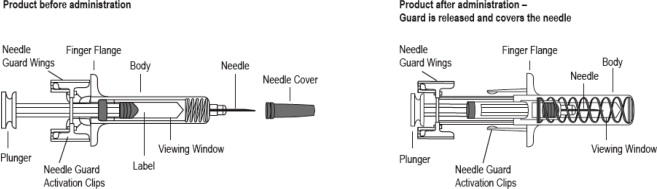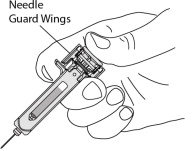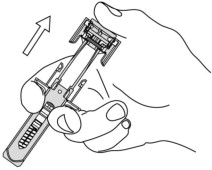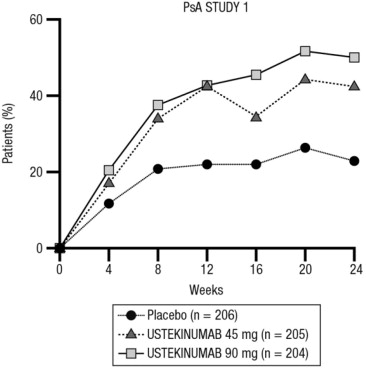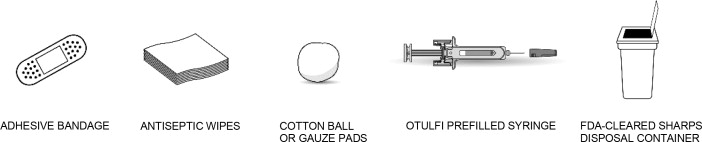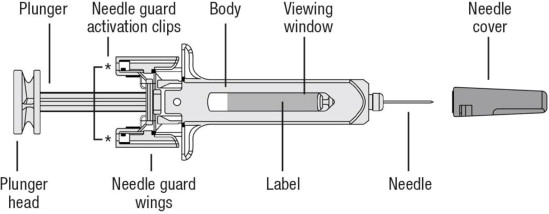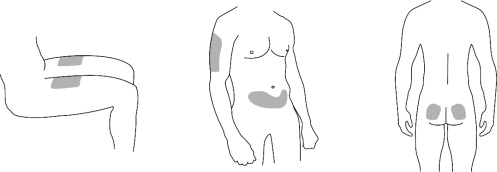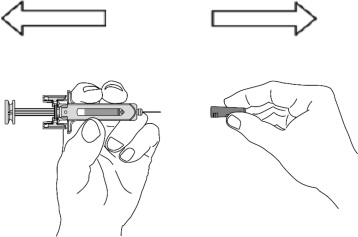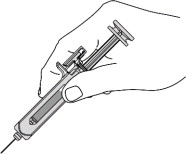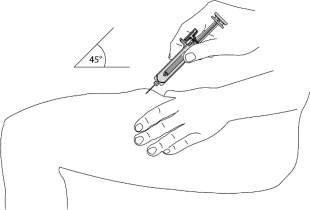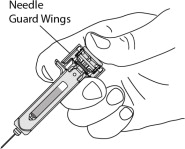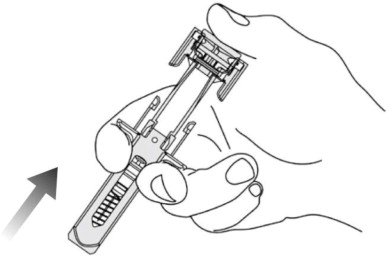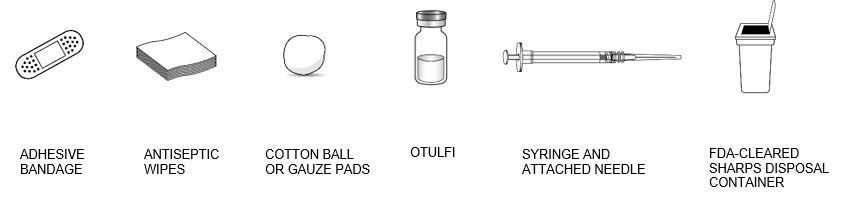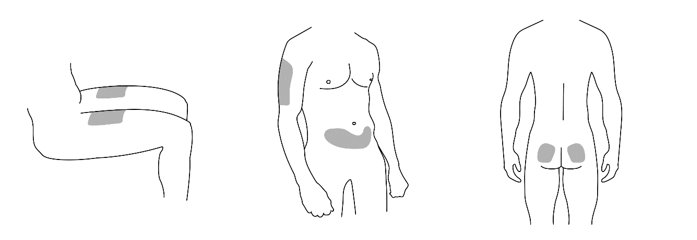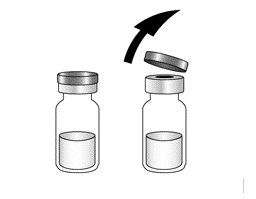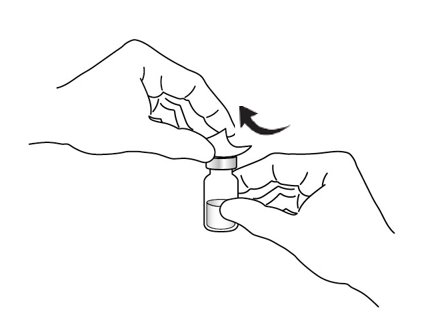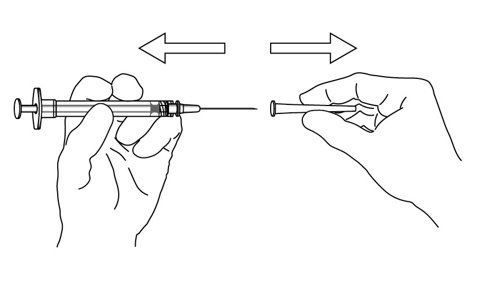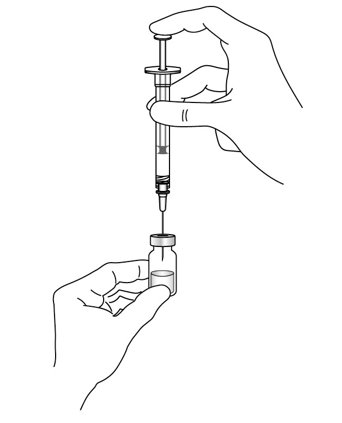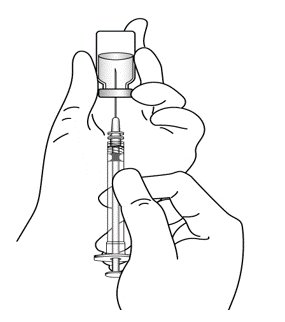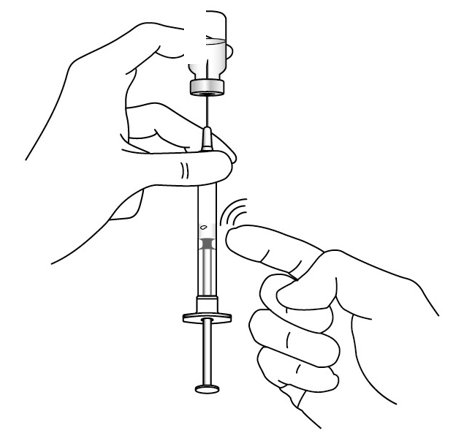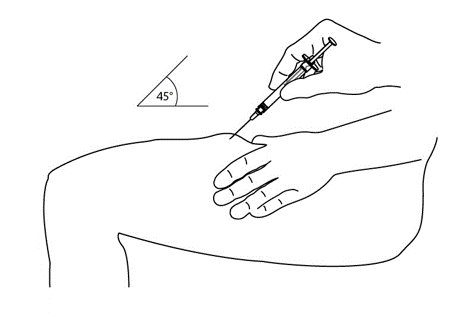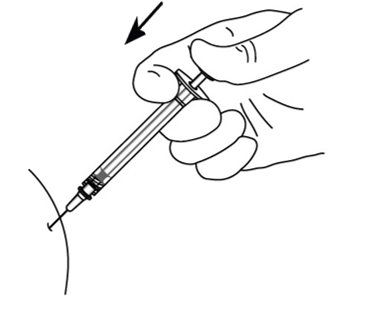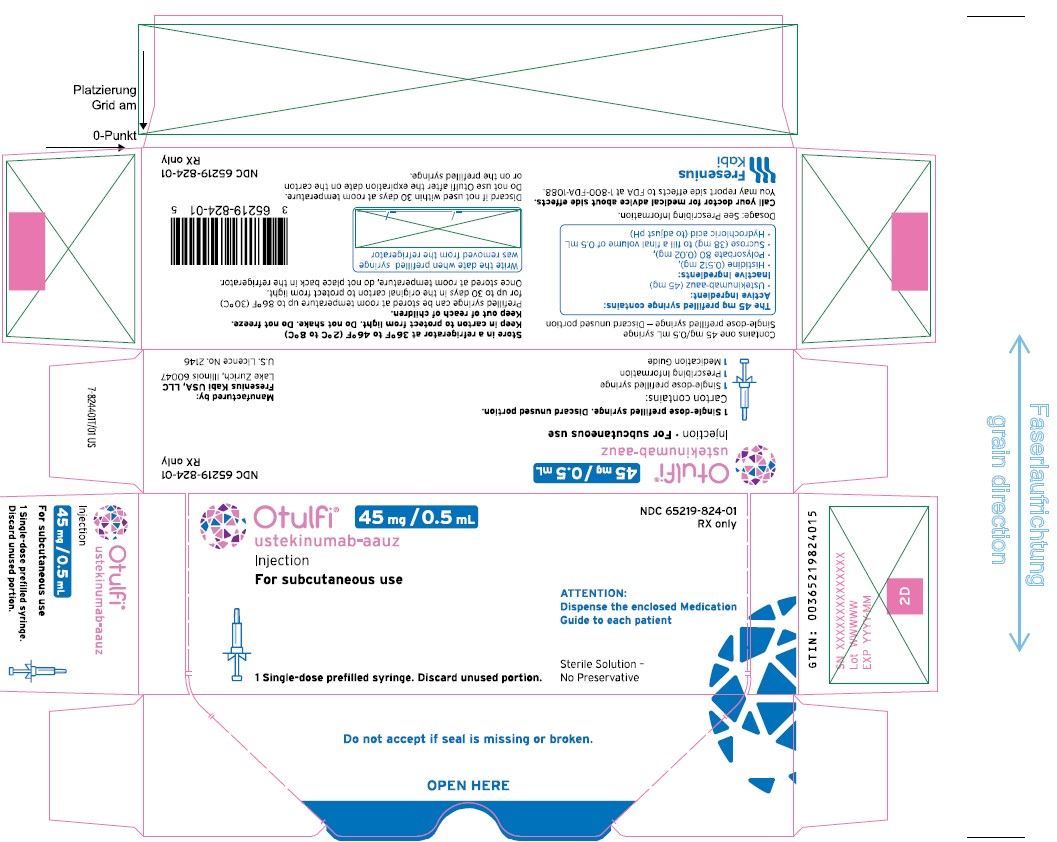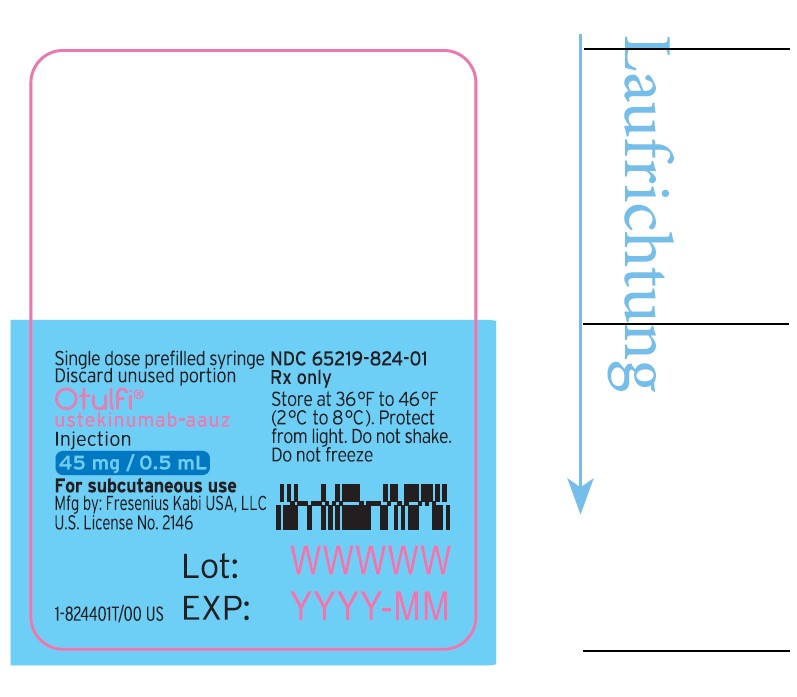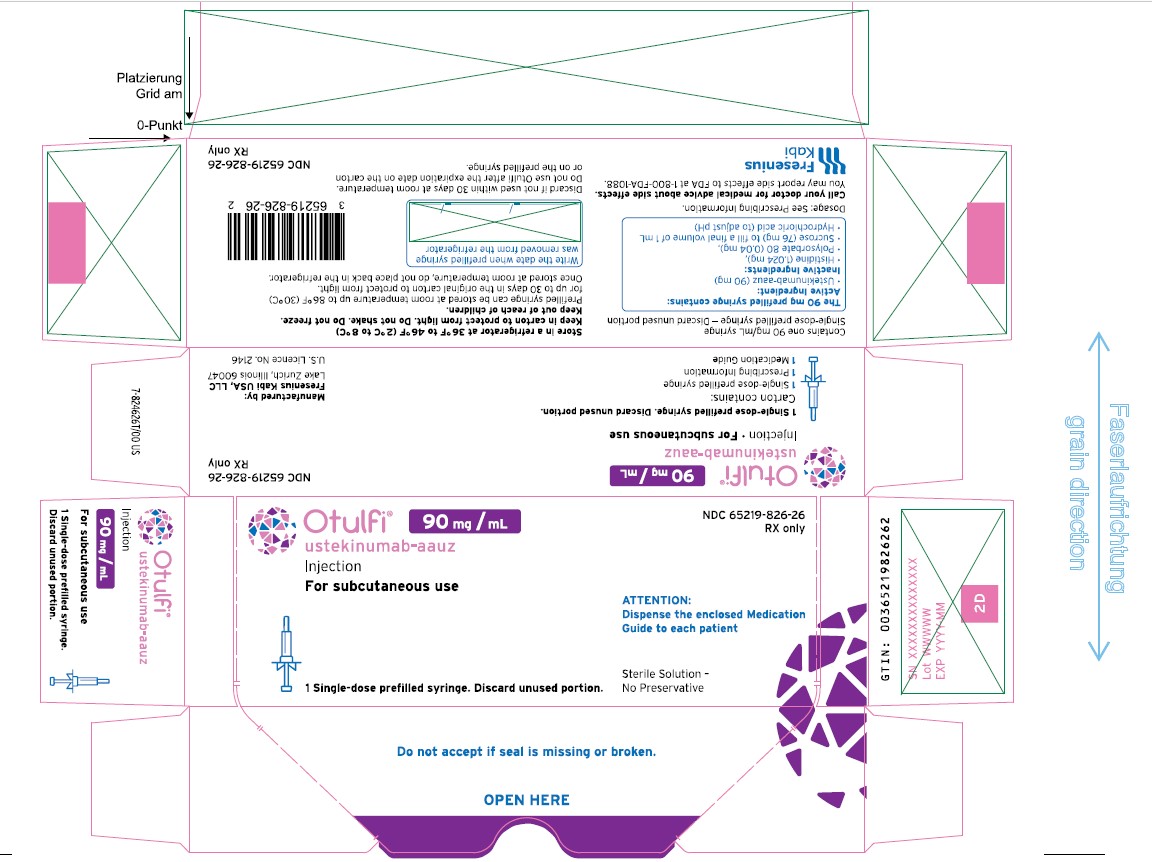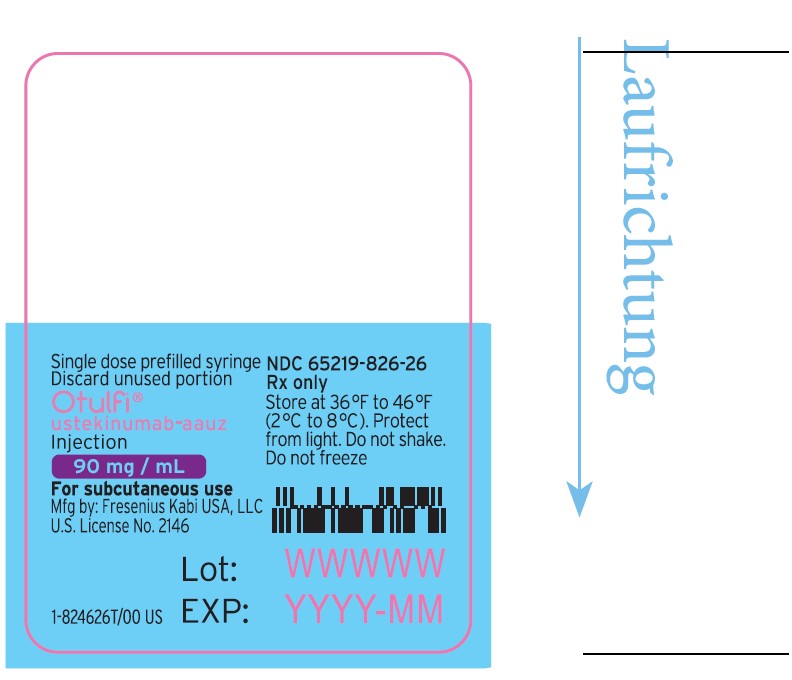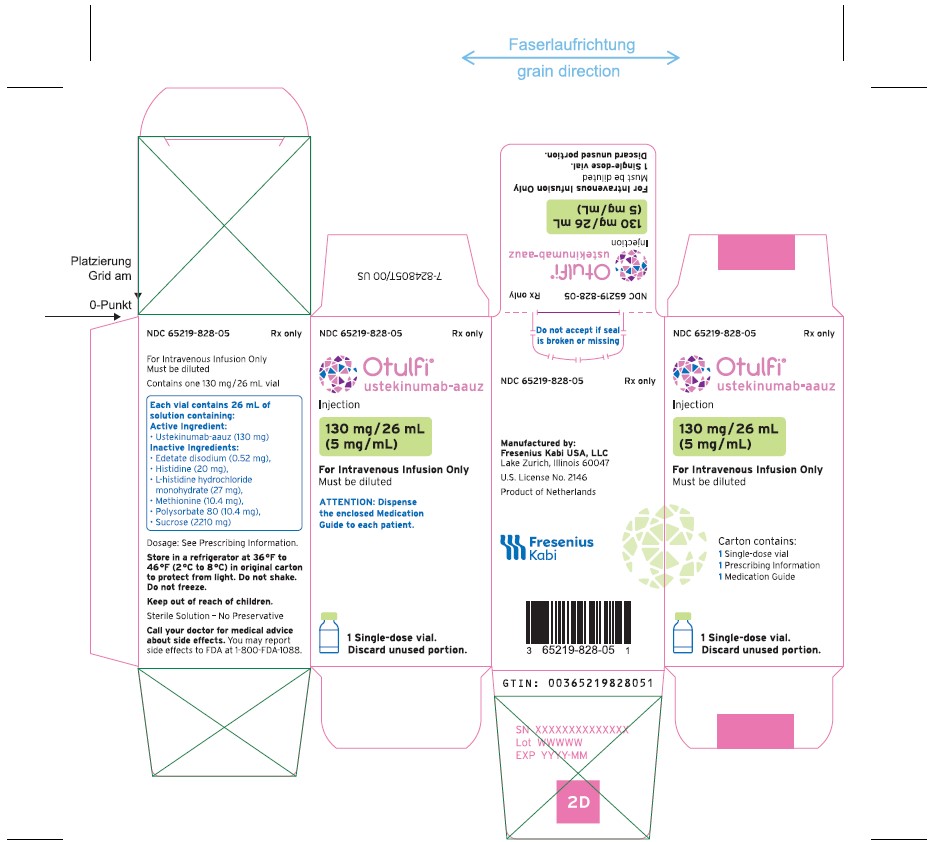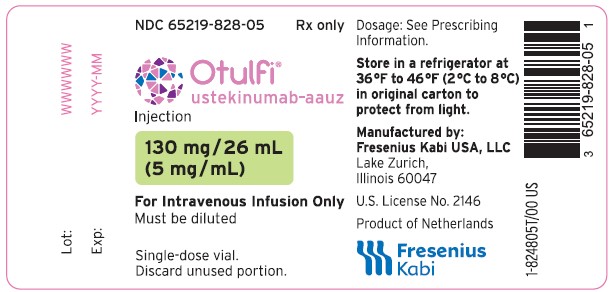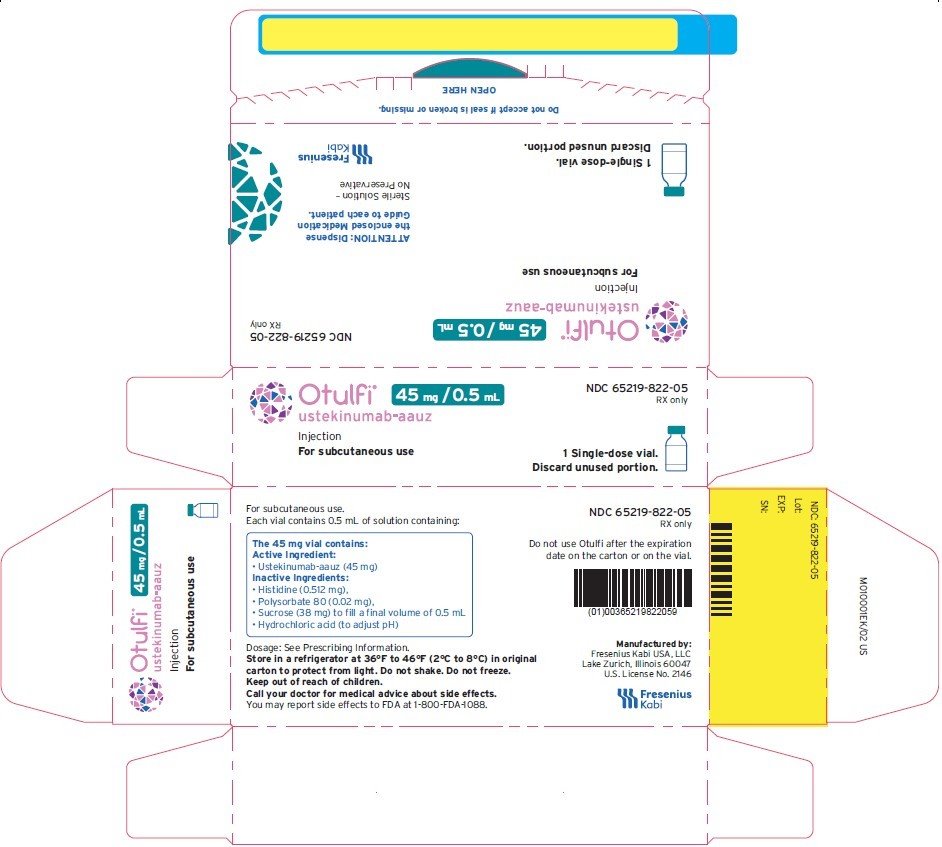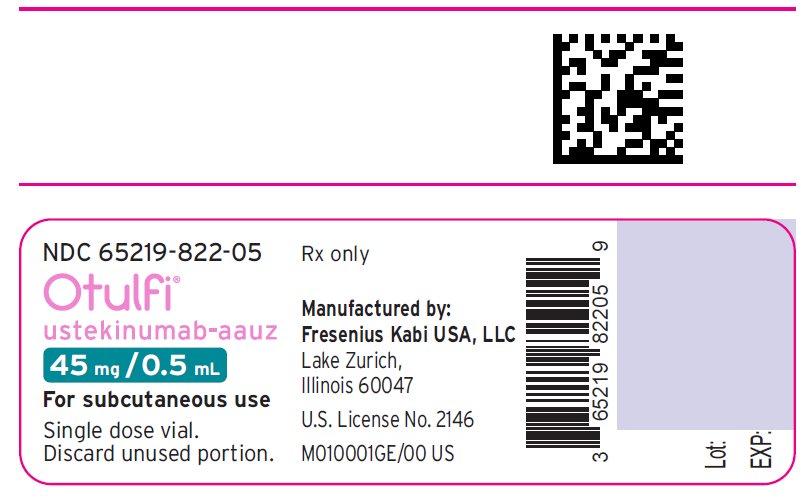 DRUG LABEL: Otulfi
NDC: 65219-824 | Form: INJECTION, SOLUTION
Manufacturer: Fresenius Kabi USA, LLC
Category: prescription | Type: HUMAN PRESCRIPTION DRUG LABEL
Date: 20251219

ACTIVE INGREDIENTS: ustekinumab 45 mg/0.5 mL
INACTIVE INGREDIENTS: histidine 0.5 mg/0.5 mL; polysorbate 80 0.02 mg/0.5 mL; sucrose 38 mg/0.5 mL; hydrochloric acid

HIGHLIGHTS OF PRESCRIBING INFORMATION

These highlights do not include all the information needed to use OTULFI safely and effectively. See full prescribing information for OTULFI.
OTULFI (ustekinumab-aauz) injection, for subcutaneous or intravenous use
Initial U.S. Approval: 2024
OTULFI (ustekinumab-aauz) is biosimilar [Biosimilar means that the biological product is approved based on data demonstrating that it is highly similar to an FDA-approved biological product, known as a reference product, and that there are no clinically meaningful differences between the biosimilar product and the reference product. Biosimilarity of OTULFI has been demonstrated for the condition(s) of use (e.g., indication(s), dosing regimen(s)), strength(s), dosage form(s), and route(s) of administration described in its Full Prescribing Information.] to STELARA ® (ustekinumab).

RECENT MAJOR CHANGES

Dosage and Administration (2.1, 2.2, 2.4) 03/2025

1 INDICATIONS AND USAGE

OTULFI is a human interleukin-12 and -23 antagonist indicated for the treatment of:

Adult patients with:

- moderate to severe plaque psoriasis (PsO) who are candidates for phototherapy or systemic therapy. (1.1)
- active psoriatic arthritis (PsA). (1.2)
- moderately to severely active Crohn's disease (CD). (1.3)
- moderately to severely active ulcerative colitis. (1.4)

Pediatric patients 6 years and older with:

- moderate to severe plaque psoriasis, who are candidates for phototherapy or systemic therapy. (1.1)
- active psoriatic arthritis (PsA). (1.2)

2 DOSAGE AND ADMINISTRATION

Psoriasis Adult Subcutaneous Recommended Dosage (2.1):

Weight Range (kilograms) | Recommended Dosage
less than or equal to 100 kg | 45 mg administered subcutaneously initially and 4 weeks later, followed by 45 mg administered subcutaneously every 12 weeks
greater than 100 kg | 90 mg administered subcutaneously initially and 4 weeks later, followed by 90 mg administered subcutaneously every 12 weeks

Psoriasis Pediatric Patients (6 to 17 years old) Subcutaneous Recommended Dosage (2.1): Weight-based dosing is recommended at the initial dose, 4 weeks later, then every 12 weeks thereafter.

Weight Range (kilograms) | Dose
less than 60 kg | 0.75 mg/kg
60 kg to 100 kg | 45 mg
greater than 100 kg | 90 mg

Psoriatic Arthritis Adult Subcutaneous Recommended Dosage (2.2):

- The recommended dosage is 45 mg administered subcutaneously initially and 4 weeks later, followed by 45 mg administered subcutaneously every 12 weeks.
- For patients with co-existent moderate-to-severe plaque psoriasis weighing greater than 100 kg, the recommended dosage is 90 mg administered subcutaneously initially and 4 weeks later, followed by 90 mg administered subcutaneously every 12 weeks.

Psoriatic Arthritis Pediatric (6 to 17 years old) Subcutaneous Recommended Dosage (2.2): Weight-based dosing is recommended at the initial dose, 4 weeks later, then every 12 weeks thereafter.

Weight Range (kilograms) | Dose
less than 60 kg | 0.75 mg/kg
60 kg or more | 45 mg
greater than 100 kg with co-existent moderate-to-severe plaque psoriasis | 90 mg

Crohn's Disease and Ulcerative Colitis Initial Adult Intravenous Recommended Dosage (2.3): A single intravenous infusion using weight- based dosing:

Weight Range (kilograms) | Dose
up to 55 kg | 260 mg (2 vials)
greater than 55 kg to 85 kg | 390 mg (3 vials)
greater than 85 kg | 520 mg (4 vials)

Crohn's Disease and Ulcerative Colitis Maintenance Adult Subcutaneous Recommended Dosage (2.3): A subcutaneous 90 mg dose 8 weeks after the initial intravenous dose, then every 8 weeks thereafter.

3 DOSAGE FORMS AND STRENGTHS

Subcutaneous Injection (3)

- Injection: 45 mg/0.5 mL or 90 mg/mL solution in a single-dose prefilled syringe
- Injection: 45 mg/0.5 mL solution in a single-dose vial

Intravenous Infusion (3)

- Injection: 130 mg/26 mL (5 mg/mL) solution in a single-dose vial (3)

4 CONTRAINDICATIONS

Clinically significant hypersensitivity to ustekinumab products or to any of the excipients in OTULFI. (4)

5 WARNINGS AND PRECAUTIONS

- Infections: Serious infections have occurred. Avoid starting OTULFI during any clinically important active infection. If a serious infection or clinically significant infection develops, discontinue OTULFI until the infection resolves. (5.1)
- Theoretical Risk for Particular Infections: Serious infections from mycobacteria, salmonella and Bacillus Calmette-Guerin (BCG) vaccinations have been reported in patients genetically deficient in IL- 12/IL-23. Consider diagnostic tests for these infections as dictated by clinical circumstances. (5.2)
- Tuberculosis (TB): Evaluate patients for TB prior to initiating treatment with OTULFI. Initiate treatment of latent TB before administering OTULFI. (5.3)
- Malignancies: Ustekinumab products may increase risk of malignancy. The safety of ustekinumab products in patients with a history of or a known malignancy has not been evaluated. (5.4)
- Hypersensitivity Reactions: If an anaphylactic or other clinically significant hypersensitivity reaction occurs, institute appropriate therapy and discontinue OTULFI. (5.5)
- Posterior Reversible Encephalopathy Syndrome (PRES): If PRES is suspected, treat promptly and discontinue OTULFI. (5.6)
- Immunizations: Avoid use of live vaccines in patients during treatment with OTULFI. (5.7)
- Noninfectious Pneumonia: Cases of interstitial pneumonia, eosinophilic pneumonia and cryptogenic organizing pneumonia have been reported during post-approval use of ustekinumab products. If diagnosis is confirmed, discontinue OTULFI and institute appropriate treatment. (5.8)

6 ADVERSE REACTIONS

Most common adverse reactions are:

- Psoriasis (≥3%): nasopharyngitis, upper respiratory tract infection, headache, and fatigue. (6.1)
- Crohn's Disease, induction (≥3%): vomiting. (6.1)
- Crohn's Disease, maintenance (≥3%): nasopharyngitis, injection site erythema, vulvovaginal candidiasis/mycotic infection, bronchitis, pruritus, urinary tract infection, and sinusitis. (6.1)
- Ulcerative colitis, induction (≥3%): nasopharyngitis (6.1)
- Ulcerative colitis, maintenance (≥3%): nasopharyngitis, headache, abdominal pain, influenza, fever, diarrhea, sinusitis, fatigue, and nausea (6.1)

To report SUSPECTED ADVERSE REACTIONS, contact Fresenius Kabi USA, LLC at 1-800-551-7176, or FDA at 1-800-FDA-1088 or www.fda.gov/medwatch.

FULL PRESCRIBING INFORMATION

1 INDICATIONS AND USAGE

1.1 Plaque Psoriasis (PsO)

OTULFI is indicated for the treatment of adults and pediatric patients 6 years of age and older with moderate to severe plaque psoriasis who are candidates for phototherapy or systemic therapy.

1.2 Psoriatic Arthritis (PsA)

OTULFI is indicated for the treatment of adults and pediatric patients 6 years of age and older with active psoriatic arthritis.

1.3 Crohn's Disease (CD)

OTULFI is indicated for the treatment of adult patients with moderately to severely active Crohn's disease.

1.4 Ulcerative Colitis

OTULFI is indicated for the treatment of adult patients with moderately to severely active ulcerative colitis.

2 DOSAGE AND ADMINISTRATION

2.1 Recommended Dosage in Plaque Psoriasis

Subcutaneous Adult Dosage Regimen

- For patients weighing 100 kg or less, the recommended dosage is 45 mg initially and 4 weeks later, followed by 45 mg every 12 weeks.
- For patients weighing more than 100 kg, the recommended dosage is 90 mg initially and 4 weeks later, followed by 90 mg every 12 weeks.

In subjects weighing more than 100 kg, 45 mg was also shown to be efficacious. However, 90 mg resulted in greater efficacy in these subjects [see Clinical Studies (14)].

Subcutaneous Pediatric Dosage Regimen

Administer OTULFI subcutaneously at Weeks 0 and 4, then every 12 weeks thereafter.

The recommended dose of OTULFI for pediatric patients (6-17 years old) with plaque psoriasis based on body weight is shown below (Table 1).

Table 1: Recommended Dose of OTULFI for Subcutaneous Injection in Pediatric Patients (6- 17 years old) with Plaque Psoriasis
Body Weight of Patient at the Time of Dosing | Recommended Dose
less than 60 kg | 0.75 mg/kg
60 kg to 100 kg | 45 mg
more than 100 kg | 90 mg
For pediatric patients weighing less than 60 kg, the administration volume for the recommended dose (0.75 mg/kg) is shown in Table 2; withdraw the appropriate volume from the single-dose vial.

Table 2: Injection volumes of OTULFI 45 mg/0.5 mL single-dose vials for pediatric patients (6- 17 years old) with plaque psoriasis and pediatric patients (6-17 years old) with psoriatic arthritis* weighing less than 60 kg
Body Weight (kg) at the time of dosing | Dose (mg) | Volume of injection (mL)
15 | 11.3 | 0.12
16 | 12.0 | 0.13
17 | 12.8 | 0.14
18 | 13.5 | 0.15
19 | 14.3 | 0.16
20 | 15.0 | 0.17
21 | 15.8 | 0.17
22 | 16.5 | 0.18
23 | 17.3 | 0.19
24 | 18.0 | 0.20
25 | 18.8 | 0.21
26 | 19.5 | 0.22
27 | 20.3 | 0.22
28 | 21.0 | 0.23
29 | 21.8 | 0.24
30 | 22.5 | 0.25
31 | 23.3 | 0.26
32 | 24 | 0.27
33 | 24.8 | 0.27
34 | 25.5 | 0.28
35 | 26.3 | 0.29
36 | 27 | 0.3
37 | 27.8 | 0.31
38 | 28.5 | 0.32
39 | 29.3 | 0.32
40 | 30 | 0.33
41 | 30.8 | 0.34
42 | 31.5 | 0.35
43 | 32.3 | 0.36
44 | 33 | 0.37
45 | 33.8 | 0.37
46 | 34.5 | 0.38
47 | 35.3 | 0.39
48 | 36 | 0.4
49 | 36.8 | 0.41
50 | 37.5 | 0.42
51 | 38.3 | 0.42
52 | 39 | 0.43
53 | 39.8 | 0.44
54 | 40.5 | 0.45
55 | 41.3 | 0.46
56 | 42 | 0.46
57 | 42.8 | 0.47
58 | 43.5 | 0.48
59 | 44.3 | 0.49

* Refer to 2.2 Psoriatic Arthritis; Subcutaneous Pediatric Dosage Regimen.

2.2 Recommended Dosage in Psoriatic Arthritis

Subcutaneous Adult Dosage Regimen

- The recommended dosage is 45 mg initially and 4 weeks later, followed by 45 mg every 12 weeks.
- For patients with co-existent moderate-to-severe plaque psoriasis weighing more than 100 kg, the recommended dosage is 90 mg initially and 4 weeks later, followed by 90 mg every 12 weeks.

Subcutaneous Pediatric Dosage Regimen

Administer OTULFI subcutaneously at Weeks 0 and 4, then every 12 weeks thereafter.

The recommended dose of OTULFI for pediatric patients (6 to 17 years old) with psoriatic arthritis, based on body weight, is shown below (Table 3).

Table 3: Recommended Dose of OTULFI for Subcutaneous Injection in Pediatric Patients (6 to 17 years old) with Psoriatic Arthritis
Body Weight of Patient at the Time of Dosing | Recommended Dose
less than 60 kg* | 0.75 mg/kg
60 kg or more | 45 mg
greater than 100 kg with co-existent moderate-to-severe plaque psoriasis | 90 mg
* For pediatric patients weighing less than 60 kg, the administration volume for the recommended dose (0.75 mg/kg) is shown in Table 2; withdraw the appropriate volume from the single-dose vial.

2.3 Recommended Dosage in Crohn's Disease and Ulcerative Colitis

Intravenous Induction Adult Dosage Regimen

A single intravenous infusion dose of OTULFI using the weight-based dosage regimen specified in Table 4 [see Instructions for dilution of OTULFI 130 mg vial for intravenous infusion (2.6)].

Table 4: Initial Intravenous Dosage of OTULFI
Body Weight of Patient at the time of dosing | Dose | Number of 130 mg/26 mL (5 mg/mL) OTULFI vials
55 kg or less | 260 mg | 2
more than 55 kg to 85 kg | 390 mg | 3
more than 85 kg | 520 mg | 4

Subcutaneous Maintenance Adult Dosage Regimen

The recommended maintenance dosage is a subcutaneous 90 mg dose administered 8 weeks after the initial intravenous dose, then every 8 weeks thereafter.

2.4 General Considerations for Administration

- OTULFI is intended for use under the guidance and supervision of a healthcare provider. OTULFI should only be administered to patients who will be closely monitored and have regular follow-up visits with a healthcare provider. The appropriate dose should be determined by a healthcare provider using the patient's current weight at the time of dosing. In pediatric patients, it is recommended that OTULFI be administered by a healthcare provider. If a healthcare provider determines that it is appropriate, a patient may self-inject or a caregiver may inject OTULFI after proper training in subcutaneous injection technique. Instruct patients to follow the directions provided in the Medication Guide [see Medication Guide].
- The needle cover on the prefilled syringe is not made with natural rubber (a derivative of latex).
- It is recommended that each injection be administered at a different anatomic location (such as upper arms, gluteal regions, thighs, or any quadrant of abdomen) than the previous injection, and not into areas where the skin is tender, bruised, erythematous, or indurated. When using the single-dose vial, a 1 mL syringe with a 27 gauge, ½ inch needle is recommended.
- Prior to administration, visually inspect OTULFI for particulate matter and discoloration. OTULFI is a clear to slightly opalescent and colorless to slightly brown-yellow solution. Do not use OTULFI if it is discolored or cloudy, or if other particulate matter is present. OTULFI does not contain preservatives; therefore, discard any unused product remaining in the vial and/or syringe.

2.5 Instructions for Administration of OTULFI Prefilled Syringes Equipped with Needle Safety Guard

Refer to the diagram below for the provided instructions.

To prevent premature activation of the needle safety guard, do not touch the NEEDLE GUARD ACTIVATION CLIPS at any time during use.

- Hold the BODY and remove the NEEDLE COVER. Do not hold the PLUNGER or PLUNGER HEAD while removing the NEEDLE COVER or the PLUNGER may move. Do not use the prefilled syringe if it is dropped without the NEEDLE COVER in place. Do not use the prefilled syringe if it is dropped or if it is dropped onto a hard surface.
- Inject OTULFI subcutaneously as recommended [see Dosage and Administration (2.1, 2.2, 2.3)].
- Inject all of the medication by pushing in the PLUNGER until the PLUNGER HEAD is completely between the needle guard wings. Injection of the entire prefilled syringe contents is necessary to activate the needle guard.
- After injection, maintain the pressure on the PLUNGER HEAD and remove the needle from the skin. Slowly take your thumb off the PLUNGER HEAD to allow the empty syringe to move up until the entire needle is covered by the needle guard, as shown by the illustration below:
- Used syringes should be placed in a puncture-resistant container.

2.6 Preparation and Administration of OTULFI 130 mg/26 mL (5 mg/mL) Vial for Intravenous Infusion (Crohn's Disease and Ulcerative Colitis)

OTULFI solution for intravenous infusion must be diluted, prepared and infused by a healthcare professional using aseptic technique.

1. Calculate the dose and the number of OTULFI vials needed based on patient weight (Table 4). Each 26 mL vial of OTULFI contains 130 mg of ustekinumab-aauz.
2. Withdraw, and then discard a volume of the 0.9% Sodium Chloride Injection, USP from the 250 mL infusion bag equal to the volume of OTULFI to be added (discard 26 mL sodium chloride for each vial of OTULFI needed, for 2 vials- discard 52 mL, for 3 vials- discard 78 mL, 4 vials- discard 104 mL). Alternatively, a 250 mL infusion bag containing 0.45% Sodium Chloride Injection, USP may be used.
3. Withdraw 26 mL of OTULFI from each vial needed and add it to the 250 mL infusion bag. The final volume in the infusion bag should be 250 mL. Gently mix.
4. Visually inspect the diluted solution before infusion. Do not use if visibly opaque particles, discoloration or foreign particles are observed.
5. Infuse the diluted solution over a period of at least one hour. Once diluted, the infusion should be completely administered within eight hours of the dilution in the infusion bag.
6. Use only polypropylene (PP) or polyvinylchloride (PVC) infusion sets with an in-line, sterile, non-pyrogenic, low protein-binding filter (pore size 0.2 micrometer).
7. Do not infuse OTULFI concomitantly in the same intravenous line with other agents.
8. OTULFI does not contain preservatives. Each vial is for one-time use in only one patient. Discard any remaining solution. Dispose any unused medicinal product in accordance with local requirements.

Storage

If necessary, the diluted infusion solution may be kept at room temperature up to 25°C (77°F) for up to 7 hours. Storage time at room temperature begins once the diluted solution has been prepared. The infusion should be completed within 8 hours after the dilution in the infusion bag (cumulative time after preparation including the storage and the infusion period). Do not freeze. Discard any unused portion of the infusion solution. Protect from light.

3 DOSAGE FORMS AND STRENGTHS

OTULFI (ustekinumab-aauz) is a clear to slightly opalescent and colorless to slightly brown-yellow solution.

Subcutaneous Injection

- Injection: 45 mg/0.5 mL or 90 mg/mL solution in a single-dose prefilled syringe
- Injection: 45 mg/0.5 mL solution in a single-dose vial

Intravenous Infusion

- Injection: 130 mg/26 mL (5 mg/mL) solution in a single-dose vial

4 CONTRAINDICATIONS

OTULFI is contraindicated in patients with clinically significant hypersensitivity to ustekinumab products or to any of the excipients in OTULFI [see Warnings and Precautions (5.5)].

5 WARNINGS AND PRECAUTIONS

5.1 Infections

Ustekinumab products may increase the risk of infections and reactivation of latent infections. Serious bacterial, mycobacterial, fungal, and viral infections were observed in patients receiving ustekinumab products [see Adverse Reactions (6.1, 6.3)].

Serious infections requiring hospitalization, or otherwise clinically significant infections, reported in clinical trials included the following:

- Plaque Psoriasis: diverticulitis, cellulitis, pneumonia, appendicitis, cholecystitis, sepsis, osteomyelitis, viral infections, gastroenteritis and urinary tract infections.
- Psoriatic arthritis: cholecystitis.
- Crohn's disease: anal abscess, gastroenteritis, ophthalmic herpes zoster, pneumonia, and listeria meningitis.
- Ulcerative colitis: gastroenteritis, ophthalmic herpes zoster, pneumonia, and listeriosis.

Avoid initiating treatment with OTULFI in patients with any clinically important active infection until the infection resolves or is adequately treated. Consider the risks and benefits of treatment prior to initiating use of OTULFI in patients with a chronic infection or a history of recurrent infection.

Instruct patients to seek medical advice if signs or symptoms suggestive of an infection occur while on treatment with OTULFI and discontinue OTULFI for serious or clinically significant infections until the infection resolves or is adequately treated.

5.2 Theoretical Risk for Vulnerability to Particular Infections

Individuals genetically deficient in IL-12/IL-23 are particularly vulnerable to disseminated infections from mycobacteria (including nontuberculous, environmental mycobacteria), salmonella (including nontyphi strains), and Bacillus Calmette-Guerin (BCG) vaccinations. Serious infections and fatal outcomes have been reported in such patients.

It is not known whether patients with pharmacologic blockade of IL-12/IL-23 from treatment with ustekinumab products may be susceptible to these types of infections. Consider appropriate diagnostic testing (e.g., tissue culture, stool culture, as dictated by clinical circumstances).

5.3 Pre-treatment Evaluation for Tuberculosis

Evaluate patients for tuberculosis infection prior to initiating treatment with OTULFI.

Avoid administering OTULFI to patients with active tuberculosis infection. Initiate treatment of latent tuberculosis prior to administering OTULFI. Consider anti-tuberculosis therapy prior to initiation of OTULFI in patients with a past history of latent or active tuberculosis in whom an adequate course of treatment cannot be confirmed. Closely monitor patients receiving OTULFI for signs and symptoms of active tuberculosis during and after treatment.

5.4 Malignancies

Ustekinumab products are immunosuppressants and may increase the risk of malignancy. Malignancies were reported among subjects who received ustekinumab in clinical trials [see Adverse Reactions (6.1)]. In rodent models, inhibition of IL-12/IL-23p40 increased the risk of malignancy [see Nonclinical Toxicology (13)].

The safety of ustekinumab products has not been evaluated in patients who have a history of malignancy or who have a known malignancy.

There have been post-marketing reports of the rapid appearance of multiple cutaneous squamous cell carcinomas in patients receiving ustekinumab products who had pre-existing risk factors for developing non-melanoma skin cancer. Monitor all patients receiving OTULFI for the appearance of non-melanoma skin cancer. Closely follow patients greater than 60 years of age, those with a medical history of prolonged immunosuppressant therapy and those with a history of PUVA treatment [see Adverse Reactions (6.1)].

5.5 Hypersensitivity Reactions

Hypersensitivity reactions, including anaphylaxis and angioedema, have been reported with ustekinumab products [see Adverse Reactions (6.1, 6.3)]. If an anaphylactic or other clinically significant hypersensitivity reaction occurs, institute appropriate therapy and discontinue OTULFI.

5.6 Posterior Reversible Encephalopathy Syndrome (PRES)

Two cases of posterior reversible encephalopathy syndrome (PRES), also known as Reversible Posterior Leukoencephalopathy Syndrome (RPLS), were reported in clinical trials. Cases have also been reported in postmarketing experience in patients with psoriasis, psoriatic arthritis and Crohn's disease. Clinical presentation included headaches, seizures, confusion, visual disturbances, and imaging changes consistent with PRES a few days to several months after ustekinumab product initiation. A few cases reported latency of a year or longer. Patients recovered with supportive care following withdrawal of ustekinumab products.

Monitor all patients treated with OTULFI for signs and symptoms of PRES. If PRES is suspected, promptly administer appropriate treatment and discontinue OTULFI.

5.7 Immunizations

Prior to initiating therapy with OTULFI, patients should receive all age-appropriate immunizations as recommended by current immunization guidelines. Patients being treated with OTULFI should avoid receiving live vaccines. Avoid administering BCG vaccines during treatment with OTULFI or for one year prior to initiating treatment or one year following discontinuation of treatment. Caution is advised when administering live vaccines to household contacts of patients receiving OTULFI because of the potential risk for shedding from the household contact and transmission to patient.

Non-live vaccinations received during a course of OTULFI may not elicit an immune response sufficient to prevent disease.

5.8 Noninfectious Pneumonia

Cases of interstitial pneumonia, eosinophilic pneumonia and cryptogenic organizing pneumonia have been reported during post-approval use of ustekinumab products. Clinical presentations included cough, dyspnea, and interstitial infiltrates following one to three doses. Serious outcomes have included respiratory failure and prolonged hospitalization. Patients improved with discontinuation of therapy and in certain cases administration of corticosteroids. If diagnosis is confirmed, discontinue OTULFI and institute appropriate treatment [see Postmarketing Experience (6.3)].

6 ADVERSE REACTIONS

The following serious adverse reactions are discussed elsewhere in the label:

- Infections [see Warnings and Precautions (5.1)]
- Malignancies [see Warnings and Precautions (5.4)]
- Hypersensitivity Reactions [see Warnings and Precautions (5.5)]
- Posterior Reversible Encephalopathy Syndrome (PRES) [see Warnings and Precautions (5.6)]
- Noninfectious Pneumonia [see Warnings and Precautions (5.8)]

6.1 Clinical Trials Experience

Because clinical trials are conducted under widely varying conditions, adverse reaction rates observed in the clinical trials of a drug cannot be directly compared to rates in the clinical trials of another drug and may not reflect the rates observed in practice.

Adult Subjects with Plaque Psoriasis

The safety data reflect exposure to ustekinumab in 3117 adult subjects with plaque psoriasis, including 2414 exposed for at least 6 months, 1855 exposed for at least one year, 1653 exposed for at least two years, 1569 exposed for at least three years, 1482 exposed for at least four years and 838 exposed for at least five years.

Table 5 summarizes the adverse reactions that occurred at a rate of at least 1% with higher rates in the ustekinumab groups during the placebo-controlled period of Ps STUDY 1 and Ps STUDY 2 [see Clinical Studies (14)].

Table 5: Adverse Reactions Reported by ≥1% of Subjects with Plaque Psoriasis and at Higher Rates in the ustekinumab groups through Week 12 in Ps STUDY 1 and Ps STUDY 2
 | ustekinumab
 | Placebo | 45 mg | 90 mg
Subjects treated | 665 | 664 | 666
Nasopharyngitis | 51 (8%) | 56 (8%) | 49 (7%)
Upper respiratory tract infection | 30 (5%) | 36 (5%) | 28 (4%)
Headache | 23 (3%) | 33 (5%) | 32 (5%)
Fatigue | 14 (2%) | 18 (3%) | 17 (3%)
Back pain | 8 (1%) | 9 (1%) | 14 (2%)
Dizziness | 8 (1%) | 8 (1%) | 14 (2%)
Pharyngolaryngeal pain | 7 (1%) | 9 (1%) | 12 (2%)
Pruritus | 9 (1%) | 10 (2%) | 9 (1%)
Injection site erythema | 3 (<1%) | 6 (1%) | 13 (2%)
Myalgia | 4 (1%) | 7 (1%) | 8 (1%)
Depression | 3 (<1%) | 8 (1%) | 4 (1%)

Adverse reactions that occurred at rates less than 1% in the controlled period of Ps STUDIES 1 and 2 through week 12 included: cellulitis, herpes zoster, diverticulitis and certain injection site reactions (pain, swelling, pruritus, induration, hemorrhage, bruising, and irritation).

One case of PRES occurred during adult plaque psoriasis clinical trials [see Warnings and Precautions (5.6)].

Infections

In the placebo-controlled period of clinical trials of subjects with plaque psoriasis (average follow-up of 12.6 weeks for placebo-treated subjects and 13.4 weeks for ustekinumab -treated subjects), 27% of ustekinumab-treated subjects reported infections (1.39 per patient-years of follow-up) compared with 24% of placebo-treated subjects (1.21 per patient-years of follow-up). Serious infections occurred in 0.3% of ustekinumab-treated subjects (0.01 per patient-years of follow-up) and in 0.4% of placebo-treated subjects (0.02 per patient-years of follow-up) [see Warnings and Precautions (5.1)].

In the controlled and non-controlled portions of plaque psoriasis clinical trials (median follow-up of 3.2 years), representing 8998 patient-years of exposure, 72.3% of ustekinumab-treated subjects reported infections (0.87 per patient-years of follow-up). Serious infections were reported in 2.8% of subjects (0.01 per patient-years of follow-up).

Malignancies

In the controlled and non-controlled portions of plaque psoriasis clinical trials (median follow-up of 3.2 years, representing 8998 patient-years of exposure), 1.7% of ustekinumab-treated subjects reported malignancies excluding non-melanoma skin cancers (0.60 per hundred patient-years of follow-up). Non-melanoma skin cancer was reported in 1.5% of ustekinumab-treated subjects (0.52 per hundred patient-years of follow-up) [see Warnings and Precautions (5.4)]. The most frequently observed malignancies other than non-melanoma skin cancer during the clinical trials were: prostate, melanoma, colorectal and breast. Malignancies other than non-melanoma skin cancer in ustekinumab-treated subjects during the controlled and uncontrolled portions of trials were similar in type and number to what would be expected in the general U.S. population according to the SEER database (adjusted for age, gender and race).^1

Pediatric Subjects with Plaque Psoriasis

The safety of ustekinumab was assessed in two trials of pediatric subjects with moderate to severe plaque psoriasis. Ps STUDY 3 evaluated safety for up to 60 weeks in 110 pediatric subjects 12 to 17 years old. Ps STUDY 4 evaluated safety for up to 56 weeks in 44 pediatric subjects 6 to 11 years old. The safety profile in pediatric subjects was similar to the safety profile from trials in adults with plaque psoriasis.

Psoriatic Arthritis

The safety of ustekinumab was assessed in 927 subjects in two randomized, double-blind, placebo- controlled trials in adults with active psoriatic arthritis (PsA). The overall safety profile of ustekinumab in subjects with PsA was consistent with the safety profile seen in adult psoriasis clinical trials. A higher incidence of arthralgia, nausea, and dental infections was observed in ustekinumab-treated subjects when compared with placebo-treated subjects (3% vs. 1% for arthralgia and 3% vs. 1% for nausea; 1% vs. 0.6% for dental infections) in the placebo-controlled portions of the PsA clinical trials.

Crohn's Disease

The safety of ustekinumab was assessed in 1407 subjects with moderately to severely active Crohn's disease (Crohn's Disease Activity Index [CDAI] greater than or equal to 220 and less than or equal to 450) in three randomized, double-blind, placebo-controlled, parallel-group, multicenter trials. These 1407 subjects included 40 subjects who received a prior investigational intravenous ustekinumab formulation but were not included in the efficacy analyses. In trials CD-1 and CD-2 there were 470 subjects who received ustekinumab 6 mg/kg as a weight-based single intravenous induction dose and 466 who received placebo [see Dosage and Administration (2.3)]. Subjects who were responders in either trial CD-1 or CD-2 were randomized to receive a subcutaneous maintenance regimen of either 90 mg ustekinumab every 8 weeks, or placebo for 44 weeks in trial CD-3. Subjects in these 3 trials may have received other concomitant therapies including aminosalicylates, immunomodulatory agents [azathioprine (AZA), 6-mercaptopurine (6-MP), methotrexate (MTX)], oral corticosteroids (prednisone or budesonide), and/or antibiotics for their Crohn's disease [see Clinical Studies (14.4)].

The overall safety profile of ustekinumab was consistent with the safety profile seen in the adult psoriasis and psoriatic arthritis clinical trials. Common adverse reactions in trials CD-1 and CD-2 and in trial CD-3 are listed in Tables 6 and 7, respectively.

Table 6: Common adverse reactions through Week 8 in Trials CD-1 and CD-2 occurring in ≥3% of ustekinumab-treated subjects and higher than placebo
 | Placebo N=466 | ustekinumab 6 mg/kg single intravenous induction dose N=470
Vomiting | 3% | 4%

Other less common adverse reactions reported in subjects in trials CD-1 and CD-2 included asthenia (1% vs 0.4%), acne (1% vs 0.4%), and pruritus (2% vs 0.4%).

Table 7: Common adverse reactions through Week 44 in Trial CD-3 occurring in ≥3% of ustekinumab-treated subjects and higher than placebo
 | Placebo; N=133 | ustekinumab 90 mg subcutaneous maintenance dose every 8 weeks N=131
Nasopharyngitis; Injection site erythema; Vulvovaginal candidiasis/mycotic infection; Bronchitis; Pruritus; Urinary tract infection; Sinusitis | 8%; 0; 1%; 3%; 2%; 2%; 2% | 11%; 5%; 5%; 5%; 4%; 4%; 3%

Infections

In subjects with Crohn's disease, serious or other clinically significant infections included anal abscess, gastroenteritis, and pneumonia. In addition, listeria meningitis and ophthalmic herpes zoster were reported in one patient each [see Warnings and Precautions (5.1)].

Malignancies

With up to one year of treatment in the Crohn's disease clinical trials, 0.2% of ustekinumab-treated subjects (0.36 events per hundred patient-years) and 0.2% of placebo-treated subjects (0.58 events per hundred patient-years) developed non-melanoma skin cancer.

Malignancies other than non-melanoma skin cancers occurred in 0.2% of ustekinumab-treated subjects (0.27 events per hundred patient-years) and in none of the placebo-treated subjects.

Hypersensitivity Reactions Including Anaphylaxis

In CD trials, two subjects reported hypersensitivity reactions following ustekinumab administration. One patient experienced signs and symptoms consistent with anaphylaxis (tightness of the throat, shortness of breath, and flushing) after a single subcutaneous administration (0.1% of subjects receiving subcutaneous ustekinumab). In addition, one subject experienced signs and symptoms consistent with or related to a hypersensitivity reaction (chest discomfort, flushing, urticaria, and increased body temperature) after the initial intravenous ustekinumab dose (0.08% of subjects receiving intravenous ustekinumab). These subjects were treated with oral antihistamines or corticosteroids and in both cases symptoms resolved within an hour.

Ulcerative Colitis

The safety of ustekinumab was evaluated in two randomized, double-blind, placebo-controlled clinical trials (UC-1 [IV induction] and UC-2 [SC maintenance]) in 960 adult subjects with moderately to severely active ulcerative colitis [see Clinical Studies (14.5)]. The overall safety profile of ustekinumab in subjects with ulcerative colitis was consistent with the safety profile seen across all approved indications. Adverse reactions reported in at least 3% of ustekinumab-treated subjects and at a higher rate than placebo were:

- Induction (UC-1): nasopharyngitis (7% vs 4%).
- Maintenance (UC-2): nasopharyngitis (24% vs 20%), headache (10% vs 4%), abdominal pain (7% vs 3%), influenza (6% vs 5%), fever (5% vs. 4%), diarrhea (4% vs 1%), sinusitis (4% vs 1%), fatigue (4% vs 2%), and nausea (3% vs 2%).

Infections

In subjects with ulcerative colitis, serious or other clinically significant infections included gastroenteritis and pneumonia. In addition, listeriosis and ophthalmic herpes zoster were reported in one subject each [see Warnings and Precautions (5.1)].

Malignancies

With up to one year of treatment in the ulcerative colitis clinical trials, 0.4% of ustekinumab-treated subjects (0.48 events per hundred patient-years) and 0.0% of placebo-treated subjects (0.00 events per hundred patient-years) developed non-melanoma skin cancer. Malignancies other than non-melanoma skin cancers occurred in 0.5% of ustekinumab-treated subjects (0.64 events per hundred patient-years) and 0.2% of placebo-treated subjects (0.40 events per hundred patient- years).

6.2 Immunogenicity

The observed incidence of anti-drug antibodies is highly dependent on the sensitivity and specificity of the assay. Differences in assay methods preclude meaningful comparisons of the incidence of anti-drug antibodies in the studies described below with the incidence of anti-drug antibodies in other studies, including those of ustekinumab or of other ustekinumab products.

Approximately 6 to 12.4% of subjects treated with ustekinumab in plaque psoriasis and psoriatic arthritis clinical trials developed antibodies to ustekinumab, which were generally low-titer. In plaque psoriasis clinical trials, antibodies to ustekinumab were associated with reduced or undetectable serum ustekinumab concentrations and reduced efficacy. In plaque psoriasis trials, the majority of subjects who were positive for antibodies to ustekinumab had neutralizing antibodies.

In Crohn's disease and ulcerative colitis clinical trials, 2.9% and 4.6% of subjects, respectively, developed antibodies to ustekinumab when treated with ustekinumab for approximately one year. No apparent association between the development of antibodies to ustekinumab and the development of injection site reactions was seen.

6.3 Postmarketing Experience

The following adverse reactions have been reported during post-approval use of ustekinumab products. Because these reactions are reported voluntarily from a population of uncertain size, it is not always possible to reliably estimate their frequency or establish a causal relationship to ustekinumab product exposure.

Immune system disorders: Serious hypersensitivity reactions (including anaphylaxis and angioedema), other hypersensitivity reactions (including rash and urticaria).

Infections and infestations: Lower respiratory tract infection (including opportunistic fungal infections and tuberculosis).

Neurological disorders: Posterior Reversible Encephalopathy Syndrome (PRES).

Respiratory, thoracic and mediastinal disorders: Interstitial pneumonia, eosinophilic pneumonia and cryptogenic organizing pneumonia.

Skin reactions: Pustular psoriasis, erythrodermic psoriasis, hypersensitivity vasculitis.

7 DRUG INTERACTIONS

7.1 Concomitant Therapies

In plaque psoriasis trials the safety of ustekinumab products in combination with immunosuppressive agents or phototherapy has not been evaluated. In psoriatic arthritis trials, concomitant MTX use did not appear to influence the safety or efficacy of ustekinumab. In Crohn's disease and ulcerative colitis induction trials, immunomodulators (6-MP, AZA, MTX) were used concomitantly in approximately 30% of subjects and corticosteroids were used concomitantly in approximately 40% and 50% of Crohn's disease and ulcerative colitis subjects, respectively. Use of these concomitant therapies did not appear to influence the overall safety or efficacy of ustekinumab.

7.2 CYP450 Substrates

The formation of CYP450 enzymes can be suppressed by increased levels of certain cytokines (e.g., IL-1, IL-6, TNFα, IFN) during chronic inflammation. Thus, use of ustekinumab products, antagonists of IL-12 and IL-23, could normalize the formation of CYP450 enzymes. Upon initiation or discontinuation of OTULFI in patients who are receiving concomitant CYP450 substrates, particularly those with a narrow therapeutic index, consider monitoring for therapeutic effect or drug concentration and adjust the individual dosage of the CYP substrateas needed See the prescribing information of specific CYP substrates.

A CYP-mediated drug interaction effect was not observed in subjects with Crohn’s disease [see Clinical Pharmacology (12.3)].

7.3 Allergen Immunotherapy

Ustekinumab products have not been evaluated in patients who have undergone allergy immunotherapy. Ustekinumab products may decrease the protective effect of allergen immunotherapy (decrease tolerance) which may increase the risk of an allergic reaction to a dose of allergen immunotherapy. Therefore, caution should be exercised in patients receiving or who have received allergen immunotherapy, particularly for anaphylaxis.

8 USE IN SPECIFIC POPULATIONS

8.1 Pregnancy

Risk Summary

Limited data from observational studies, published case reports, and postmarketing surveillance on the use of ustekinumab products during pregnancy are insufficient to inform a drug associated risk of major birth defects, miscarriage, and other adverse maternal or fetal outcomes. Transport of human IgG antibody across the placenta increases as pregnancy progresses and peaks during the third trimester; therefore, ustekinumab products may be transferred to the developing fetus (see Clinical Considerations). In animal reproductive and developmental toxicity studies, no adverse developmental effects were observed in offspring after administration of ustekinumab to pregnant monkeys at exposures greater than 100 times the maximum recommended human dose (MRHD).

The background risk of major birth defects and miscarriage for the indicated population(s) are unknown. All pregnancies have a background risk of birth defect, loss, or other adverse outcomes. In the U.S. general population, the estimated background risk of major birth defects and miscarriage of clinically recognized pregnancies is 2% to 4% and 15% to 20%, respectively.

Clinical Considerations

Fetal/Neonatal Adverse Reactions

Because ustekinumab products may theoretically interfere with immune response to infections, consider risks and benefits prior to administering live vaccines to infants exposed to OTULFI in utero. There are insufficient data regarding exposed infant serum levels of ustekinumab products at birth and the duration of persistence of ustekinumab products in infant serum after birth. Although a specific timeframe to delay administration of live attenuated vaccines in infants exposed in utero is unknown, consider the risks and benefits of delaying a minimum of 6 months after birth because of the clearance of the product.

Data

Animal Data

Ustekinumab was tested in two embryo-fetal development toxicity studies in cynomolgus monkeys. No teratogenic or other adverse developmental effects were observed in fetuses from pregnant monkeys that were administered ustekinumab subcutaneously twice weekly or intravenously weekly during the period of organogenesis. Serum concentrations of ustekinumab in pregnant monkeys were greater than 100 times the serum concentration in patients treated subcutaneously with 90 mg of ustekinumab weekly for 4 weeks.

In a combined embryo-fetal development and pre- and post-natal development toxicity study, pregnant cynomolgus monkeys were administered subcutaneous doses of ustekinumab twice weekly at exposures greater than 100 times the MRHD from the beginning of organogenesis to Day 33 after delivery. Neonatal deaths occurred in the offspring of one monkey administered ustekinumab at 22.5 mg/kg and one monkey dosed at 45 mg/kg. No ustekinumab-related effects on functional, morphological, or immunological development were observed in the neonates from birth through six months of age.

8.2 Lactation

Risk Summary

Limited data from published literature suggests that ustekinumab is present in human breast milk. There are no available data on the effects of ustekinumab products on milk production. The effects of local gastrointestinal exposure and limited systemic exposure in the breastfed infant to ustekinumab products are unknown. No adverse effects on the breastfed infant causally related to ustekinumab products have been identified in the published literature or postmarketing experience.

The developmental and health benefits of breastfeeding should be considered along with the mother's clinical need for OTULFI and any potential adverse effects on the breastfed child from OTULFI or from the underlying maternal condition.

8.4 Pediatric Use

Plaque Psoriasis

The safety and effectiveness of OTULFI have been established for the treatment of moderate to severe plaque psoriasis in pediatric patients 6 to 17 years of age who are candidates for phototherapy or systemic therapy.

Use of OTULFI in pediatric patients 12 to less than 17 years of age is supported by evidence from a multicenter, randomized, 60-week trial (Ps STUDY 3) of ustekinumab that included a 12-week, double-blind, placebo-controlled, parallel-group portion, in 110 pediatric subjects 12 years of age and older [see Adverse Reactions (6.1), Clinical Studies (14.2)].

Use of OTULFI in pediatric patients 6 to 11 years of age is supported by evidence from an open-label, single-arm, efficacy, safety and pharmacokinetics trial (Ps STUDY 4) of ustekinumab in 44 subjects [see Adverse Reactions (6.1), Pharmacokinetics (12.3)].

The safety and effectiveness of OTULFI have not been established in pediatric patients less than 6 years of age with plaque psoriasis.

Psoriatic Arthritis

The safety and effectiveness of OTULFI have been established for treatment of psoriatic arthritis in pediatric patients 6 to 17 years old.

Use of OTULFI in these age groups is supported by evidence from adequate and well controlled trials of ustekinumab in adults with psoriasis and PsA, pharmacokinetic data from adult subjects with psoriasis, adult subjects with PsA and pediatric subjects with psoriasis, and safety data of ustekinumab from two clinical trials in 44 pediatric subjects 6 to 11 years old with psoriasis and 110 pediatric subjects 12 to 17 years old with psoriasis. The observed pre-dose (trough) concentrations are generally comparable between adult subjects with psoriasis, adult subjects with PsA and pediatric subjects with psoriasis, and the PK exposure is expected to be comparable between adult and pediatric subjects with PsA [see Adverse Reactions (6.1), Clinical Pharmacology (12.3), and Clinical Studies (14.1, 14.2, 14.3)].

The safety and effectiveness of OTULFI have not been established in pediatric patients less than 6 years old with psoriatic arthritis.

Crohn's Disease and Ulcerative Colitis

The safety and effectiveness of OTULFI have not been established in pediatric patients with Crohn's disease or ulcerative colitis.

8.5 Geriatric Use

Of the 6709 subjects exposed to ustekinumab, a total of 340 were 65 years of age or older (183 subjects with plaque psoriasis, 65 subjects with psoriatic arthritis, 58 subjects with Crohn’s disease and 34 subjects with ulcerative colitis), and 40 subjects were 75 years of age or older. Clinical trials of ustekinumab did not include sufficient numbers of subjects 65 years of age and older to determine whether they respond differently from younger adult subjects.

10 OVERDOSAGE

Single doses up to 6 mg/kg intravenously have been administered in clinical trials without dose-limiting toxicity. In case of overdosage, monitor the patient for any signs or symptoms of adverse reactions or effects and institute appropriate symptomatic treatment immediately. Consider contacting the Poison Help line (1-800-222-1222) or a medical toxicologist for additional overdose management recommendations.

11 DESCRIPTION

Ustekinumab-aauz, a human IgG1κ monoclonal antibody, is a human interleukin-12 and -23 antagonist. Using DNA recombinant technology, ustekinumab-aauz is produced in a Chinese hamster ovary (CHO) cell line. The manufacturing process contains steps for the clearance of viruses. Ustekinumab-aauz is comprised of 1326 amino acids and has an estimated molecular mass that ranges from 148,079 to 149,690 Daltons.

OTULFI (ustekinumab-aauz) injection is a sterile, preservative-free, clear to slightly opalescent, and colorless to slightly brown-yellow solution with pH of 5.7- 6.3.

OTULFI for Subcutaneous Use

Available as 45 mg of ustekinumab-aauz in 0.5 mL and 90 mg of ustekinumab-aauz in 1 mL, supplied as a sterile solution in a single-dose prefilled syringe with a 29 gauge fixed ½ inch needle and as 45 mg of ustekinumab in 0.5 mL in a single-dose 3 mL Type I glass with a coated stopper. The syringe is fitted with a passive needle guard and a needle cover that is not made with natural rubber (latex).

Each 0.5 mL prefilled syringe or vial delivers 45 mg ustekinumab-aauz, histidine (0.512 mg), Polysorbate 80 (0.02 mg), sucrose (38 mg) and hydrochloric acid (to adjust pH).

Each 1 mL prefilled syringe delivers 90 mg ustekinumab-aauz, histidine (1.024 mg), Polysorbate 80 (0.04 mg), sucrose (76 mg) and hydrochloric acid (to adjust pH).

OTULFI for Intravenous Infusion

Available as 130 mg of ustekinumab-aauz in 26 mL, supplied as a single-dose 30 mL Type I glass vial with a coated stopper.

Each 26 mL vial delivers 130 mg ustekinumab-aauz, edetate disodium (0.47 mg), histidine (20 mg), L-histidine hydrochloride monohydrate (27 mg), methionine (10.4 mg), Polysorbate 80 (10.4 mg) and sucrose (2210 mg).

12 CLINICAL PHARMACOLOGY

12.1 Mechanism of Action

Ustekinumab products are human IgG1қ monoclonal antibodies that bind with specificity to the p40 protein subunit used by both the IL-12 and IL-23 cytokines. IL-12 and IL-23 are naturally occurring cytokines that are involved in inflammatory and immune responses, such as natural killer cell activation and CD4+ T-cell differentiation and activation. In in vitro models, ustekinumab products were shown to disrupt IL-12 and IL-23 mediated signaling and cytokine cascades by disrupting the interaction of these cytokines with a shared cell-surface receptor chain, IL-12Rβ1. The cytokines IL-12 and IL-23 have been implicated as important contributors to the chronic inflammation that is a hallmark of Crohn's disease and ulcerative colitis. In animal models of colitis, genetic absence or antibody blockade of the p40 subunit of IL-12 and IL-23, the target of ustekinumab products was shown to be protective.

12.2 Pharmacodynamics

Plaque Psoriasis

In a small exploratory trial, a decrease was observed in the expression of mRNA of its molecular targets IL-12 and IL-23 in lesional skin biopsies measured at baseline and up to two weeks post-treatment in subjects with plaque psoriasis.

Ulcerative Colitis

In both trial UC-1 (induction) and trial UC-2 (maintenance), a positive relationship was observed between exposure and rates of clinical remission, clinical response, and endoscopic improvement. The response rate approached a plateau at the ustekinumab exposures associated with the recommended dosing regimen for maintenance treatment [see Clinical Studies (14.5)].

12.3 Pharmacokinetics

Absorption

In adult subjects with plaque psoriasis, the median time to reach the maximum serum concentration (Tmax) was 13.5 days and 7 days, respectively, after a single subcutaneous administration of 45 mg (N=22) and 90 mg (N=24) of ustekinumab. In healthy subjects (N=30), the median Tmax value (8.5 days) following a single subcutaneous administration of 90 mg of ustekinumab was comparable to that observed in subjects with plaque psoriasis.

Following multiple subcutaneous doses of ustekinumab in adult subjects with plaque psoriasis, steady- state serum concentrations of ustekinumab were achieved by Week 28. The mean (±SD) steady- state trough serum ustekinumab concentrations were 0.69 ± 0.69 mcg/mL for subjects less than or equal to 100 kg receiving a 45 mg dose and 0.74 ± 0.78 mcg/mL for subjects greater than 100 kg receiving a 90 mg dose. There was no apparent accumulation in serum ustekinumab concentration over time when given subcutaneously every 12 weeks.

Following the recommended intravenous induction dose, mean ±SD peak serum ustekinumab concentration was 125.2 ± 33.6 mcg/mL in subjects with Crohn's disease, and 129.1 ± 27.6 mcg/mL in subjects with ulcerative colitis. Starting at Week 8, the recommended subcutaneous maintenance dosing of 90 mg ustekinumab was administered every 8 weeks. Steady state ustekinumab concentration was achieved by the start of the second maintenance dose. There was no apparent accumulation in ustekinumab concentration over time when given subcutaneously every 8 weeks. Mean ±SD steady-state trough concentration was 2.5 ± 2.1 mcg/mL in subjects with Crohn's disease, and 3.3 ± 2.3 mcg/mL in subjects with ulcerative colitis for 90 mg ustekinumab administered every 8 weeks.

Distribution

Population pharmacokinetic analyses showed that the volume of distribution of ustekinumab in the central compartment was 2.7 L (95% CI: 2.69, 2.78) in subjects with Crohn's disease and 3.0 L (95% CI: 2.96, 3.07) in subjects with ulcerative colitis. The total volume of distribution at steady- state was 4.6 L in subjects with Crohn's disease and 4.4 L in subjects with ulcerative colitis.

Elimination

The mean (±SD) half-life ranged from 14.9 ± 4.6 to 45.6 ± 80.2 days across all plaque psoriasis trials following subcutaneous administration. Population pharmacokinetic analyses showed that the clearance of ustekinumab was 0.19 L/day (95% CI: 0.185, 0.197) in subjects with Crohn's disease and 0.19 L/day (95% CI: 0.179, 0.192) in subjects with ulcerative colitis with an estimated median terminal half-life of approximately 19 days for both IBD (Crohn's disease and ulcerative colitis) populations.

These results indicate the pharmacokinetics of ustekinumab were similar between subjects with Crohn's disease and ulcerative colitis.

Metabolism

The metabolic pathway of ustekinumab products has not been characterized. As a human IgG1ϰ monoclonal antibody, ustekinumab products are expected to be degraded into small peptides and amino acids via catabolic pathways in the same manner as endogenous IgG.

Specific Populations

Weight

When given the same dose, subjects with plaque psoriasis or psoriatic arthritis weighing more than 100 kg had lower median serum ustekinumab concentrations compared with those subjects weighing 100 kg or less. The median trough serum concentrations of ustekinumab in subjects of higher weight (greater than 100 kg) in the 90 mg group were comparable to those in subjects of lower weight (100 kg or less) in the 45 mg group.

Age: Geriatric Population

A population pharmacokinetic analysis (N=106/1937 subjects with plaque psoriasis greater than or equal to 65 years old) was performed to evaluate the effect of age on the pharmacokinetics of ustekinumab. There were no apparent changes in pharmacokinetic parameters (clearance and volume of distribution) in subjects older than 65 years old.

Age: Pediatric Population

Following multiple recommended doses of ustekinumab in pediatric subjects 6 to 17 years of age with plaque psoriasis, steady-state serum concentrations of ustekinumab were achieved by Week 28. At Week 28, the mean ±SD steady-state trough serum ustekinumab concentrations were 0.36 ± 0.26 mcg/mL and 0.54 ± 0.43 mcg/mL, respectively, in pediatric subjects 6 to 11 years of age and pediatric subjects 12 to 17 years of age.

Overall, the observed steady state ustekinumab trough concentrations in pediatric subjects with plaque psoriasis were within the range of those observed for adult subjects with plaque psoriasis and adult subjects with PsA after administration of ustekinumab.

Drug Interaction Studies

The effects of IL-12 or IL-23 on the regulation of CYP450 enzymes were evaluated in an in vitro study using human hepatocytes, which showed that IL-12 and/or IL-23 at levels of 10 ng/mL did not alter human CYP450 enzyme activities (CYP1A2, 2B6, 2C9, 2C19, 2D6, or 3A4).

No clinically significant changes in exposure of caffeine (CYP1A2 substrate), warfarin (CYP2C9 substrate), omeprazole (CYP2C19 substrate), dextromethorphan (CYP2D6 substrate), or midazolam (CYP3A substrate) were observed when used concomitantly with ustekinumab at the approved recommended dosage in subjects with Crohn’s disease. [see Drug Interactions (7.2)].

Population pharmacokinetic analyses indicated that the clearance of ustekinumab was not impacted by concomitant MTX, NSAIDs, and oral corticosteroids, or prior exposure to a TNF blocker in subjects with psoriatic arthritis.

In subjects with Crohn's disease and ulcerative colitis, population pharmacokinetic analyses did not indicate changes in ustekinumab clearance with concomitant use of corticosteroids or immunomodulators (AZA, 6-MP, or MTX); and serum ustekinumab concentrations were not impacted by concomitant use of these medications.

13 NONCLINICAL TOXICOLOGY

13.1 Carcinogenesis, Mutagenesis, Impairment of Fertility

Animal studies have not been conducted to evaluate the carcinogenic or mutagenic potential of ustekinumab products. Published literature showed that administration of murine IL-12 caused an anti- tumor effect in mice that contained transplanted tumors and IL-12/IL-23p40 knockout mice or mice treated with anti-IL-12/IL-23p40 antibody had decreased host defense to tumors. Mice genetically manipulated to be deficient in both IL-12 and IL-23 or IL-12 alone developed UV- induced skin cancers earlier and more frequently compared to wild-type mice. The relevance of these experimental findings in mouse models for malignancy risk in humans is unknown.

No effects on fertility were observed in male cynomolgus monkeys that were administered ustekinumab at subcutaneous doses up to 45 mg/kg twice weekly (45 times the MRHD on a mg/kg basis) prior to and during the mating period. However, fertility and pregnancy outcomes were not evaluated in mated females.

No effects on fertility were observed in female mice that were administered an analogous IL-12/IL-23p40 antibody by subcutaneous administration at doses up to 50 mg/kg, twice weekly, prior to and during early pregnancy.

13.2 Animal Toxicology and/or Pharmacology

In a 26-week toxicology study, one out of 10 monkeys subcutaneously administered 45 mg/kg ustekinumab twice weekly for 26 weeks had a bacterial infection.

14 CLINICAL STUDIES

14.1 Adult Plaque Psoriasis

Two multicenter, randomized, double-blind, placebo-controlled trials (Ps STUDY 1 and Ps STUDY 2) enrolled a total of 1996 subjects 18 years of age and older with plaque psoriasis who had a minimum body surface area involvement of 10%, and Psoriasis Area and Severity Index (PASI) score ≥12, and who were candidates for phototherapy or systemic therapy. Subjects with guttate, erythrodermic, or pustular psoriasis were excluded from the trials.

Ps STUDY 1 enrolled 766 subjects and Ps STUDY 2 enrolled 1230 subjects. The trials had the same design through Week 28. In both trials, subjects were randomized in equal proportion to placebo, 45 mg or 90 mg of ustekinumab. Subjects randomized to ustekinumab received 45 mg or 90 mg doses, regardless of weight, at Weeks 0, 4, and 16. Subjects randomized to receive placebo at Weeks 0 and 4 crossed over to receive ustekinumab (either 45 mg or 90 mg) at Weeks 12 and 16.

In both trials, subjects in all treatment groups had a median baseline PASI score ranging from approximately 17 to 18. Baseline PGA score was marked or severe in 44% of subjects in Ps STUDY 1 and 40% of subjects in Ps STUDY 2. Approximately two-thirds of all subjects had received prior phototherapy, 69% had received either prior conventional systemic or biologic therapy for the treatment of psoriasis, with 56% receiving prior conventional systemic therapy and 43% receiving prior biologic therapy. A total of 28% of subjects had a history of psoriatic arthritis.

In both trials, the endpoints were the proportion of subjects who achieved at least a 75% reduction in PASI score (PASI 75) from baseline to Week 12 and treatment success (cleared or minimal) on the Physician's Global Assessment (PGA). The PGA is a 6-category scale ranging from 0 (cleared) to 5 (severe) that indicates the physician's overall assessment of psoriasis focusing on plaque thickness/induration, erythema, and scaling.

Clinical Response

The results of Ps STUDY 1 and Ps STUDY 2 are presented in Table 8 below.

Table 8: Clinical Outcomes at Week 12 in Adults with Plaque Psoriasis in Ps STUDY 1 and Ps STUDY 2
 | Ps STUDY 1; ustekinumab |  |  | Ps STUDY 2; ustekinumab
 | Placebo | 45 mg | 90 mg | Placebo | 45 mg | 90 mg
Subjects randomized | 255 | 255 | 256 | 410 | 409 | 411
PASI 75 response | 8 (3%) | 171 (67%) | 170 (66%) | 15 (4%) | 273 (67%) | 311 (76%)
PGA of Cleared or Minimal | 10 (4%) | 151 (59%) | 156 (61%) | 18 (4%) | 277 (68%) | 300 (73%)

Examination of age, gender, and race subgroups did not identify differences in response to ustekinumab among these subgroups.

In subjects who weighed 100 kg or less, response rates were comparable with both the 45 mg and 90 mg doses; however, in subjects who weighed greater than 100 kg, higher response rates were seen with 90 mg dosing compared with 45 mg dosing (Table 9 below).

Table 9: Clinical Outcomes by Weight at Week 12 in Adults with Plaque Psoriasis in Ps STUDY 1 and Ps STUDY 2
 | Ps STUDY 1; ustekinumab |  |  | Ps STUDY 2; ustekinumab
 | Placebo | 45 mg | 90 mg | Placebo | 45 mg | 90 mg
Subjects randomized | 255 | 255 | 256 | 410 | 409 | 411
PASI 75 response | 255 | 255 | 256 | 410 | 409 | 411
≤100 kg | 4%; 6/166 | 74%; 124/168 | 65%; 107/164 | 4%; 12/290 | 73%; 218/297 | 78%; 225/289
>100 kg | 2%; 2/89 | 54%; 47/87 | 68%; 63/92 | 3%; 3/120 | 49%; 55/112 | 71%; 86/121
PGA of Cleared or Minimal
≤100 kg | 4%; 7/166 | 64%; 108/168 | 63%; 103/164 | 5%; 14/290 | 74%; 220/297 | 75%; 216/289
>100 kg | 3%; 3/89 | 49%; 43/87 | 58%; 53/92 | 3%; 4/120 | 51%; 57/112 | 69%; 84/121
* Subjects were dosed with trial medication at Weeks 0 and 4.

Subjects in Ps STUDY 1 who were PASI 75 responders at both Weeks 28 and 40 were re- randomized at Week 40 to either continued dosing of ustekinumab (ustekinumab at Week 40) or to withdrawal of therapy (placebo at Week 40). At Week 52, 89% (144/162) of subjects re- randomized to ustekinumab treatment were PASI 75 responders compared with 63% (100/159) of subjects re-randomized to placebo (treatment withdrawal after Week 28 dose). The median time to loss of PASI 75 response among the subjects randomized to treatment withdrawal was 16 weeks.

14.2 Pediatric Plaque Psoriasis

A multicenter, randomized, double blind, placebo-controlled trial (Ps STUDY 3) enrolled 110 pediatric subjects 12 to 17 years of age with a minimum BSA involvement of 10%, a PASI score greater than or equal to 12, and a PGA score greater than or equal to 3, who were candidates for phototherapy or systemic therapy and whose disease was inadequately controlled by topical therapy.

Subjects were randomized to receive placebo (n = 37), the recommended dose of ustekinumab (n = 36), or one-half the recommended dose of ustekinumab (n = 37) by subcutaneous injection at Weeks 0 and 4 followed by dosing every 12 weeks (q12w). The recommended dose of ustekinumab was 0.75 mg/kg for subjects weighing less than 60 kg, 45 mg for subjects weighing 60 kg to 100 kg, and 90 mg for subjects weighing greater than 100 kg. At Week 12, subjects who received placebo were crossed over to receive ustekinumab at the recommended dose or one-half the recommended dose.

Of the pediatric subjects, approximately 63% had prior exposure to phototherapy or conventional systemic therapy and approximately 11% had prior exposure to biologics.

The endpoints were the proportion of subjects who achieved a PGA score of cleared (0) or minimal (1), PASI 75, and PASI 90 at Week 12. Subjects were followed for up to 60 weeks following first administration of trial agent.

Clinical Response

The efficacy results at Week 12 for Ps STUDY 3 are presented in Table 10.

Table 10: Efficacy Results at Week 12 in Pediatric Subjects 12 to 17 years with Plaque Psoriasis in Ps STUDY 3
Ps STUDY 3 | Placebo n (%) | ustekinumab * n (%)
N | 37 | 36
PGA
PGA of cleared (0) or minimal (1) | 2 (5.4%) | 25 (69.4%)
PASI
PASI 75 responders | 4 (10.8%) | 29 (80.6%)
PASI 90 responders | 2 (5.4%) | 22 (61.1%)
* Using the weight-based dosage regimen specified in Table 1 and Table 2

14.3 Psoriatic Arthritis

The safety and efficacy of ustekinumab was assessed in 927 subjects (PsA STUDY 1, n=615; PsA STUDY 2, n=312), in two randomized, double-blind, placebo-controlled trials in adult subjects 18 years of age and older with active PsA (≥5 swollen joints and ≥5 tender joints) despite non-steroidal anti-inflammatory (NSAID) or disease modifying antirheumatic (DMARD) therapy. Subjects in these trials had a diagnosis of PsA for at least 6 months. Subjects with each subtype of PsA were enrolled, including polyarticular arthritis with the absence of rheumatoid nodules (39%), spondylitis with peripheral arthritis (28%), asymmetric peripheral arthritis (21%), distal interphalangeal involvement (12%) and arthritis mutilans (0.5%). Over 70% and 40% of the subjects, respectively, had enthesitis and dactylitis at baseline.

Subjects were randomized to receive treatment with ustekinumab 45 mg, 90 mg, or placebo subcutaneously at Weeks 0 and 4 followed by every 12 weeks (q12w) dosing. Approximately 50% of subjects continued on stable doses of MTX (≤25 mg/week). The primary endpoint was the percentage of subjects achieving ACR 20 response at Week 24.

In PsA STUDY 1 and PsA STUDY 2, 80% and 86% of the subjects, respectively, had been previously treated with DMARDs. In PsA STUDY 1, previous treatment with anti-tumor necrosis factor (TNF)-α agent was not allowed. In PsA STUDY 2, 58% (n=180) of the subjects had been previously treated with TNF blocker, of whom over 70% had discontinued their TNF blocker treatment for lack of efficacy or intolerance at any time.

Clinical Response

In both trials, a greater proportion of subjects achieved ACR 20, ACR 50 and PASI 75 response in the ustekinumab 45 mg and 90 mg groups compared to placebo at Week 24 (see Table 11). ACR 70 responses were also higher in the ustekinumab 45 mg and 90 mg groups, although the difference was only numerical (p=NS) in STUDY 2. Responses were consistent in subjects treated with ustekinumab alone or in combination with methotrexate. Responses were similar in subjects regardless of prior TNFα exposure.

Table 11: ACR 20, ACR 50, ACR 70 and PASI 75 responses in PsA STUDY 1 and PsA STUDY 2 at Week 24
 | PsA STUDY 1; ustekinumab |  |  | PsA STUDY 2; ustekinumab
 | Placebo | 45 mg | 90 mg | Placebo | 45 mg | 90 mg
Number of subjects
randomized | 206 | 205 | 204 | 104 | 103 | 105
ACR 20 response, N (%) | 47 (23%) | 87 (42%) | 101 (50%) | 21 (20%) | 45 (44%) | 46 (44%)
ACR 50 response, N (%) | 18 (9%) | 51 (25%) | 57 (28%) | 7 (7%) | 18 (17%) | 24 (23%)
ACR 70 response, N | 5 (2%) | 25 (12%) | 29 (14%) | 3 (3%) | 7 (7%) | 9 (9%)
Number of subjects with
≥ 3% BSAa | 146 | 145 | 149 | 80 | 80 | 81
PASI 75 response, N (%) | 16 (11%) | 83 (57%) | 93 (62%) | 4 (5%) | 41 (51%) | 45 (56%)
a Number of subjects with ≥ 3% BSA psoriasis skin involvement at baseline

The percent of subjects achieving ACR 20 responses by visit is shown in Figure 1.

Figure 1: Percent of subjects achieving ACR 20 response through Week 24

The results of the components of the ACR response criteria are shown in Table 12.

Table 12: Mean change from baseline in ACR components at Week 24
 |  | PsA STUDY 1
 | ustekinumab
 | Placebo (N = 206) | 45 mg (N = 205) | 90 mg (N = 204)
Number of swollen jointsa
Baseline | 15 | 12 | 13
Mean Change at Week 24 | -3 | -5 | -6
Number of tender jointsb
Baseline | 25 | 22 | 23
Mean Change at Week 24 | -4 | -8 | -9
Subject’s assessment of painc
Baseline | 6.1 | 6.2 | 6.6
Mean Change at Week 24 | -0.5 | -2.0 | -2.6
Subject global assessmentc
Baseline | 6.1 | 6.3 | 6.4
Mean Change at Week 24 | -0.5 | -2.0 | -2.5
Physician global assessmentc
Baseline | 5.8 | 5.7 | 6.1
Mean Change at Week 24 | -1.4 | -2.6 | -3.1
Disability index (HAQ)d
Baseline | 1.2 | 1.2 | 1.2
Mean Change at Week 24 | -0.1 | -0.3 | -0.4
CRP (mg/dL)e
Baseline | 1.6 | 1.7 | 1.8
Mean Change at Week 24 | 0.01 | -0.5 | -0.8
a Number of swollen joints counted (0-66)
b Number of tender joints counted (0-68)
c Visual analogue scale; 0= best, 10=worst.
d Disability Index of the Health Assessment Questionnaire; 0 = best, 3 = worst, measures the patient's ability to perform the following: dress/groom, arise, eat, walk, reach, grip, maintain hygiene, and maintain daily activity.
e CRP: (Normal Range 0.0-1.0 mg/dL)

An improvement in enthesitis and dactylitis scores was observed in each ustekinumab group compared with placebo at Week 24.

Physical Function

Ustekinumab-treated subjects showed improvement in physical function compared to subjects treated with placebo as assessed by HAQ-DI at Week 24. In both trials, the proportion of HAQ- DI responders (≥0.3 improvement in HAQ-DI score) was greater in the ustekinumab 45 mg and 90 mg groups compared to placebo at Week 24.

14.4 Crohn's Disease

Ustekinumab was evaluated in three randomized, double-blind, placebo-controlled clinical trials in adult subjects with moderately to severely active Crohn's disease (Crohn's Disease Activity Index [CDAI] score of 220 to 450). There were two 8-week intravenous induction trials (CD-1 and CD-2) followed by a 44-week subcutaneous randomized withdrawal maintenance trial (CD-3) representing 52 weeks of therapy. Subjects in CD-1 had failed or were intolerant to treatment with one or more TNF blockers, while subjects in CD-2 had failed or were intolerant to treatment with immunomodulators or corticosteroids, but never failed treatment with a TNF blocker.

Trials CD-1 and CD-2

In trials CD-1 and CD-2, 1409 subjects were randomized, of whom 1368 (CD-1, n=741; CD-2, n=627) were included in the final efficacy analysis. Induction of clinical response (defined as a reduction in CDAI score of greater than or equal to 100 points or CDAI score of less than 150) at Week 6 and clinical remission (defined as a CDAI score of less than 150) at Week 8 were evaluated. In both trials, subjects were randomized to receive a single intravenous administration of ustekinumab at either approximately 6 mg/kg, placebo (see Table 4), or 130 mg (a lower dose than recommended).

In trial CD-1, subjects had failed or were intolerant to prior treatment with a TNF blocker: 29% subjects had an inadequate initial response (primary non-responders), 69% responded but subsequently lost response (secondary non-responders) and 36% were intolerant to a TNF blocker. Of these subjects, 48% failed or were intolerant to one TNF blocker and 52% had failed 2 or 3 prior TNF blockers. At baseline and throughout the trial, approximately 46% of the subjects were receiving corticosteroids and 31% of the subjects were receiving immunomodulators (AZA, 6-MP, MTX). The median baseline CDAI score was 319 in the ustekinumab approximately 6 mg/kg group and 313 in the placebo group.

In trial CD-2, subjects had failed or were intolerant to prior treatment with corticosteroids (81% of subjects), at least one immunomodulator (6-MP, AZA, MTX; 68% of subjects), or both (49% of subjects). Additionally, 69% never received a TNF blocker and 31% previously received but had not failed a TNF blocker. At baseline, and throughout the trial, approximately 39% of the subjects were receiving corticosteroids and 35% of the subjects were receiving immunomodulators (AZA, 6-MP, MTX). The median baseline CDAI score was 286 in the ustekinumab and 290 in the placebo group.

In these induction trials, a greater proportion of subjects treated with ustekinumab (at the recommended dose of approximately 6 mg/kg dose) achieved clinical response at Week 6 and clinical remission at Week 8 compared to placebo (see Table 13 for clinical response and remission rates). Clinical response and remission were significant as early as Week 3 in ustekinumab-treated subjects and continued to improve through Week 8.

Table 13: Induction of Clinical Response and Remission in CD-1* and CD-2**
 | CD-1 n = 741 |  |  | CD-2 n = 627
 | Placebo N = 247 | ustekinumab † N = 249 | Treatment difference and 95% CI | Placebo N = 209 | ustekinumab † N = 209 | Treatment difference and 95% CI
Clinical Response (100 point), Week 6 | 53 (21%) | 84 (34%)a | 12% (4%, 20%) | 60 (29%) | 116 (56%)b | 27% (18%, 36%)
Clinical Remission, Week 8 | 18 (7%) | 52 (21%)b | 14% (8%, 20%) | 41 (20%) | 84 (40%)b | 21% (12%, 29%)
Clinical Response (100 point), Week 8 | 50 (20%) | 94 (38%)b | 18% (10%, 25%) | 67 (32%) | 121 (58%)b | 26% (17%, 35%)
70 Point Response, Week 6 | 75 (30%) | 109 (44%)a | 13% (5%, 22%) | 81 (39%) | 135 (65%)b | 26% (17%, 35%)
70 Point Response, Week 3 | 67 (27%) | 101 (41%)a | 13% (5%, 22%) | 66 (32%) | 106 (51%)b | 19% (10%, 28%)
Clinical remission is defined as CDAI score < 150; Clinical response is defined as reduction in CDAI score by at least 100 points or being in clinical remission: 70 point response is defined as reduction in CDAI score by at least 70 points
* Patient population consisted of subjects who failed or were intolerant to TNF blocker therapy
** Patient population consisted of subjects who failed or were intolerant to corticosteroids or immunomodulators (e.g., 6-MP, AZA, MTX) and previously received but not failed a TNF blocker or were never treated with a TNF blocker.
† Infusion dose of ustekinumab using the weight-based dosage regimen specified in Table 3.
a 0.001≤ p < 0.01
b p < 0.001

Trial CD-3

The maintenance trial (CD-3) evaluated 388 subjects who achieved clinical response (≥100-point reduction in CDAI score) at Week 8 with either induction dose of ustekinumab in trials CD-1 or CD-2. Subjects were randomized to receive a subcutaneous maintenance regimen of either 90 mg ustekinumab every 8 weeks or placebo for 44 weeks (see Table 14).

Table 14: Clinical Response and Remission in CD-3 (Week 44; 52 weeks from initiation of the induction dose)
 | Placebo* N = 131† | 90 mg ustekinumab every 8 weeks N = 128† | Treatment difference and 95% CI
Clinical Remission | 47 (36%) | 68 (53%)a | 17% (5%, 29%)
Clinical Response | 58 (44%) | 76 (59%)b | 15% (3%, 27%)
Clinical Remission in subjects in remission at the start of maintenance therapy** | 36/79 (46%) | 52/78 (67%)a | 21% (6%, 36%)
Clinical remission is defined as CDAI score < 150; Clinical response is defined as reduction in CDAI of at least 100 points or being in clinical remission
* The placebo group consisted of subjects who were in response to ustekinumab and were randomized to receive placebo at the start of maintenance therapy.
** subjects in remission at the end of maintenance therapy who were in remission at the start of maintenance therapy. This does not account for any other time point during maintenance therapy.
† subjects who achieved clinical response to ustekinumab at the end of the induction trial.
a p < 0.01
b 0.01≤ p < 0.05

At Week 44, 47% of subjects who received ustekinumab were corticosteroid-free and in clinical remission, compared to 30% of subjects in the placebo group.

At Week 0 of trial CD-3, 34/56 (61%) ustekinumab-treated subjects who previously failed or were intolerant to TNF blocker therapies were in clinical remission and 23/56 (41%) of these subjects were in clinical remission at Week 44. In the placebo arm, 27/61 (44%) subjects were in clinical remission at Week 0 while 16/61 (26%) of these subjects were in remission at Week 44.

At Week 0 of trial CD-3, 46/72 (64%) ustekinumab-treated subjects who had previously failed immunomodulator therapy or corticosteroids (but not TNF blockers) were in clinical remission and 45/72 (63%) of these subjects were in clinical remission at Week 44. In the placebo arm, 50/70 (71%) of these subjects were in clinical remission at Week 0 while 31/70 (44%) were in remission at Week 44. In the subset of these subjects who were also naïve to TNF blockers, 34/52 (65%) of ustekinumab-treated subjects were in clinical remission at Week 44 as compared to 25/51 (49%) in the placebo arm.

Subjects who were not in clinical response 8 weeks after ustekinumab induction were not included in the primary efficacy analyses for trial CD-3; however, these subjects were eligible to receive a 90 mg subcutaneous injection of ustekinumab upon entry into trial CD-3. Of these subjects, 102/219 (47%) achieved clinical response eight weeks later and were followed for the duration of the trial.

14.5 Ulcerative Colitis

Ustekinumab was evaluated in two randomized, double-blind, placebo-controlled clinical trials [UC-1 and UC-2 (NCT02407236)] in adult subjects with moderately to severely active ulcerative colitis who had an inadequate response to or failed to tolerate a biologic (i.e., TNF blocker and/or vedolizumab), corticosteroids, and/or 6-MP or AZA therapy. The 8-week intravenous induction trial (UC-1) was followed by the 44-week subcutaneous randomized withdrawal maintenance trial (UC-2) for a total of 52 weeks of therapy.

Disease assessment was based on the Mayo score, which ranged from 0 to 12 and has four subscores that were each scored from 0 (normal) to 3 (most severe): stool frequency, rectal bleeding, findings on centrally reviewed endoscopy, and physician global assessment. Moderately to severely active ulcerative colitis was defined at baseline (Week 0) as Mayo score of 6 to 12, including a Mayo endoscopy subscore ≥2. An endoscopy score of 2 was defined by marked erythema, absent vascular pattern, friability, erosions; and a score of 3 was defined by spontaneous bleeding, ulceration. At baseline, subjects had a median Mayo score of 9, with 84% of subjects having moderate disease (Mayo score 6-10) and 15% having severe disease (Mayo score 11-12).

Subjects in these trials may have received other concomitant therapies including aminosalicylates, immunomodulatory agents (AZA, 6-MP, or MTX), and oral corticosteroids (prednisone).

Trial UC-1

In UC-1, 961 subjects were randomized at Week 0 to a single intravenous administration of ustekinumab of approximately 6 mg/kg, 130 mg (a lower dose than recommended), or placebo. Subjects enrolled in UC-1 had to have failed therapy with corticosteroids, immunomodulators or at least one biologic. A total of 51% had failed at least one biologic and 17% had failed both a TNF blocker and an integrin receptor blocker. Of the total population, 46% had failed corticosteroids or immunomodulators but were biologic-naïve and an additional 3% had previously received but had not failed a biologic. At induction baseline and throughout the trial, approximately 52% subjects were receiving oral corticosteroids, 28% subjects were receiving immunomodulators (AZA, 6-MP, or MTX) and 69% subjects were receiving aminosalicylates.

The primary endpoint was clinical remission at Week 8. Clinical remission with a definition of: Mayo stool frequency subscore of 0 or 1, Mayo rectal bleeding subscore of 0 (no rectal bleeding), and Mayo endoscopy subscore of 0 or 1 (Mayo endoscopy subscore of 0 defined as normal or inactive disease and Mayo subscore of 1 defined as presence of erythema, decreased vascular pattern and no friability) is provided in Table 15.

The secondary endpoints were clinical response, endoscopic improvement, and histologic- endoscopic mucosal improvement. Clinical response with a definition of (≥ 2 points and ≥ 30% decrease in modified Mayo score, defined as 3-component Mayo score without the Physician's Global Assessment, with either a decrease from baseline in the rectal bleeding subscore ≥1 or a rectal bleeding subscore of 0 or 1), endoscopic improvement with a definition of Mayo endoscopy subscore of 0 or 1, and histologic-endoscopic mucosal improvement with a definition of combined endoscopic improvement and histologic improvement of the colon tissue [neutrophil infiltration in <5% of crypts, no crypt destruction, and no erosions, ulcerations, or granulation tissue]) are provided in Table 14.

In UC-1, a significantly greater proportion of subjects treated with ustekinumab (at the recommended dose of approximately 6 mg/kg dose) were in clinical remission and response and achieved endoscopic improvement and histologic-endoscopic mucosal improvement compared to placebo (see Table 15).

Table 15: Proportion of Subjects Meeting Efficacy Endpoints at Week 8 in UC-1
Endpoint | Placebo N = 319 |  | ustekinumab † N = 322 |  | Treatment difference and 97.5% CI a
Endpoint | N | % | N | %
Clinical Remission* | 22 | 7% | 62 | 19% | 12% (7%, 18%) b
Bio-naïve⸸ | 14/151 | 9% | 36/147 | 24%
Prior biologic failure | 7/161 | 4% | 24/166 | 14%
Endoscopic Improvement§ | 40 | 13% | 80 | 25% | 12% (6%, 19%) b
Bio-naïve⸸ | 28/151 | 19% | 43/147 | 29%
Prior biologic failure | 11/161 | 7% | 34/166 | 20%
Clinical Response† | 99 | 31% | 186 | 58% | 27% (18%, 35%) b
Bio-naïve⸸ | 55/151 | 36% | 94/147 | 64%
Prior biologic failure | 42/161 | 26% | 86/166 | 52%
Histologic-Endoscopic Mucosal Improvement‡ | 26 | 8% | 54 | 17% | 9% (3%, 14%) b
Bio-naïve⸸ | 19/151 | 13% | 30/147 | 20%
Prior biologic failure | 6/161 | 4% | 21/166 | 13%
† Infusion dose of ustekinumab using the weight-based dosage regimen specified in Table 3.
⸸ An additional 7 subjects on placebo and 9 subjects on ustekinumab (6 mg/kg) had been exposed to, but had not failed, biologics.
* Clinical remission was defined as Mayo stool frequency subscore of 0 or 1, Mayo rectal bleeding subscore of 0, and Mayo endoscopy subscore of 0 or 1 (modified so that 1 does not include friability).
§ Endoscopic improvement was defined as Mayo endoscopy subscore of 0 or 1 (modified so that 1 does not include friability).
† Clinical response was defined as a decrease from baseline in the modified Mayo score by ≥30% and ≥2 points, with either a decrease from baseline in the rectal bleeding subscore ≥1 or a rectal bleeding subscore of 0 or 1.
‡ Histologic-endoscopic mucosal improvement was defined as combined endoscopic improvement (Mayo endoscopy subscore of 0 or 1) and histologic improvement of the colon tissue (neutrophil infiltration in <5% of crypts, no crypt destruction, and no erosions, ulcerations, or granulation tissue).
a Adjusted treatment difference (97.5% CI)
b p < 0.001

The relationship of histologic-endoscopic mucosal improvement, as defined in UC-1, at Week 8 to disease progression and long-term outcomes was not evaluated during UC-1.

Rectal Bleeding and Stool Frequency Subscores

Decreases in rectal bleeding and stool frequency subscores were observed as early as Week 2 in ustekinumab-treated subjects.

Trial UC-2

The maintenance trial (UC-2) evaluated 523 subjects who achieved clinical response 8 weeks following the intravenous administration of either induction dose of ustekinumab in UC-1. These subjects were randomized to receive a subcutaneous maintenance regimen of either 90 mg ustekinumab every 8 weeks, or every 12 weeks (a lower dose than recommended), or placebo for 44 weeks.

The primary endpoint was the proportion of subjects in clinical remission at Week 44. The secondary endpoints included the proportion of subjects maintaining clinical response at Week 44, the proportion of subjects with endoscopic improvement at Week 44, the proportion of subjects with corticosteroid-free clinical remission at Week 44, and the proportion of subjects maintaining clinical remission at Week 44 among subjects who achieved clinical remission 8 weeks after induction.

Results of the primary and secondary endpoints at Week 44 in subjects treated with ustekinumab at the recommended dosage (90 mg every 8 weeks) compared to the placebo are shown in Table 16.

Table 16: Efficacy Endpoints of Maintenance at Week 44 in UC-2 (52 Weeks from Initiation of the Induction Dose)
Endpoint | Placebo* N = 175† |  | 90 mg ustekinumab every 8 weeks N = 176 |  | Treatment difference and 95% CI
Endpoint | N | % | N | %
Clinical Remission** | 46 | 26% | 79 | 45% | 19% (9%, 28%) a
Bio-naïve⸸ | 30/84 | 36% | 39/79 | 49%
Prior biologic failure | 16/88 | 18% | 37/91 | 41%
Maintenance of Clinical Response at Week 44† | 84 | 48% | 130 | 74% | 26% (16%, 36%) a
Bio-naïve⸸ | 49/84 | 58% | 62/79 | 78%
Prior biologic failure | 35/88 | 40% | 64/91 | 70%
Endoscopic Improvement§ | 47 | 27% | 83 | 47% | 20% (11%, 30%) a
Bio-naïve⸸ | 29/84 | 35% | 42/79 | 53%
Prior biologic failure | 18/88 | 20% | 38/91 | 42%
Corticosteroid-free Clinical Remission‡ | 45 | 26% | 76 | 43% | 17% (8%, 27%) a
Bio-naïve⸸ | 30/84 | 36% | 38/79 | 48%
Prior biologic failure | 15/88 | 17% | 35/91 | 38%
Maintenance of Clinical Remission at Week 44 in subjects who achieved clinical remission 8 weeks after induction | 18/50 | 36% | 27/41 | 66% | 31% (12%, 50%) b
Bio-naïve⸸ | 12/27 | 44% | 14/20 | 70%
Prior biologic failure | 6/23 | 26% | 12/18 | 67%
⸸ An additional 3 subjects on placebo and 6 subjects on ustekinumab had been exposed to, but had not failed, biologics.
* The placebo group consisted of subjects who were in response to ustekinumab and were randomized to receive placebo at the start of maintenance therapy.
** Clinical remission was defined as Mayo stool frequency subscore of 0 or 1, Mayo rectal bleeding subscore of 0, and Mayo endoscopy subscore of 0 or 1 (modified so that 1 does not include friability).
† Clinical response was defined as a decrease from baseline in the modified Mayo score by ≥30% and ≥2 points, with either a decrease from baseline in the rectal bleeding subscore ≥1 or a rectal bleeding subscore of 0 or 1.
§ Endoscopic improvement was defined as Mayo endoscopy subscore of 0 or 1 (modified so that 1 does not include friability).
‡ Corticosteroid-free clinical remission was defined as subjects in clinical remission and not receiving corticosteroids at Week 44.
a p =<0.001
b p=0.004

Other Endpoints

Week 16 Responders to Ustekinumab Induction

Subjects who were not in clinical response 8 weeks after induction with ustekinumab in UC-1 were not included in the primary efficacy analyses for trial UC-2; however, these subjects were eligible to receive a 90 mg subcutaneous injection of ustekinumab at Week 8. Of these subjects, 55/101 (54%) achieved clinical response eight weeks later (Week 16) and received ustekinumab 90 mg subcutaneously every 8 weeks during the UC-2 trial. At Week 44, there were 97/157 (62%) subjects who maintained clinical response and there were 51/157 (32%) who achieved clinical remission.

Histologic-Endoscopic Mucosal Improvement at Week 44

The proportion of subjects achieving histologic-endoscopic mucosal improvement during maintenance treatment in UC-2 was 75/172 (44%) among subjects on ustekinumab and 40/172 (23%) in subjects on placebo at Week 44. The relationship of histologic-endoscopic mucosal improvement, as defined in UC-2, at Week 44 to progression of disease or long-term outcomes was not evaluated in UC-2.

Endoscopic Normalization

Normalization of endoscopic appearance of the mucosa was defined as a Mayo endoscopic subscore of 0. At Week 8 in UC-1, endoscopic normalization was achieved in 25/322 (8%) of subjects treated with ustekinumab and 12/319 (4%) of subjects in the placebo group. At Week 44 of UC-2, endoscopic normalization was achieved in 51/176 (29%) of subjects treated with ustekinumab and in 32/175 (18%) of subjects in placebo group.

15 REFERENCES

1. Surveillance, Epidemiology, and End Results (SEER) Program (www.seer.cancer.gov) SEER*Stat Database: Incidence - SEER 6.6.2 Regs Research Data, Nov 2009 Sub (1973- 2007) - Linked To County Attributes - Total U.S., 1969-2007 Counties, National Cancer Institute, DCCPS, Surveillance Research Program, Surveillance Systems Branch, released April 2010, based on the November 2009 submission.

16 HOW SUPPLIED/STORAGE AND HANDLING

OTULFI (ustekinumab-aauz) injection is a sterile, preservative-free, clear to slightly opalescent and colorless to slightly brown-yellow solution. It is supplied as individually packaged, single-dose prefilled syringes or single-dose vials.

For Subcutaneous Use

Prefilled Syringes

- 45 mg/0.5 mL (NDC 65219-824-01)
- 90 mg/mL (NDC 65219-826-26)

Each prefilled syringe is equipped with a 29 gauge fixed ½ inch needle, a needle safety guard, and a needle cover that is not made with natural rubber

Single-dose Vial

- 45 mg/0.5 mL (NDC 65219-822-05)

For Intravenous Infusion

Single-dose Vial

- 130 mg/26 mL (5 mg/mL) (NDC 65219-828-05)

Storage and Stability

Store OTULFI vials and prefilled syringes refrigerated between 2ºC to 8ºC (36ºF to 46ºF). Store OTULFI vials upright. Keep the product in the original carton to protect from light until the time of use. Do not freeze. Do not shake.

If needed, individual prefilled syringes may be stored at room temperature up to 30°C (86°F) for a maximum single period of up to 30 days in the original carton to protect from light. Record the date when the prefilled syringe is first removed from the refrigerator on the carton in the space provided. Once a syringe has been stored at room temperature, do not return to the refrigerator. Discard the syringe if not used within 30 days at room temperature storage. Do not use OTULFI after the expiration date on the carton or on the prefilled syringe.

17 PATIENT COUNSELING INFORMATION

Advise the patient and/or caregiver to read the FDA-approved patient labeling (Medication Guide and Instructions for Use).

Infections

Inform patients that OTULFI may lower the ability of their immune system to fight infections and to contact their healthcare provider immediately if they develop any signs or symptoms of infection [see Warnings and Precautions (5.1)].

Malignancies

Inform patients of the risk of developing malignancies while receiving OTULFI [see Warnings and Precautions (5.4)].

Hypersensitivity Reactions

- Advise patients to seek immediate medical attention if they experience any signs or symptoms of serious hypersensitivity reactions and discontinue OTULFI [see Warnings and Precautions (5.5)].

Posterior Reversible Encephalopathy Syndrome (PRES)

Inform patients to immediately contact their healthcare provider if they experience signs and symptoms of PRES (which may include headache, seizures, confusion, or visual disturbances) [see Warnings and Precautions (5.6)].

Immunizations

Inform patients that OTULFI can interfere with the usual response to immunizations and that they should avoid live vaccines [see Warnings and Precautions (5.7)].

Administration

Instruct patients to follow sharps disposal recommendations, as described in the Instructions for Use.

Manufactured by: Fresenius Kabi USA, LLC, Lake Zurich, IL 60047, U.S.A, US License Number 2146

MEDICATION GUIDE
OTULFI [oh tool fee]
(ustekinumab-aauz)
injection, for subcutaneous or intravenous use

What is the most important information I should know about OTULFI?
OTULFI is a medicine that affects your immune system. OTULFI can increase your risk of having serious side effects, including:
Serious infections. OTULFI may lower the ability of your immune system to fight infections and may increase your risk of infections. Some people have serious infections while taking ustekinumab products, including tuberculosis (TB), and infections caused by bacteria, fungi, or viruses. Some people have to be hospitalized for treatment of their infection.

- Your doctor should check you for TB before starting OTULFI.
- If your doctor feels that you are at risk for TB, you may be treated with medicine for TB before you begin treatment with OTULFI and during treatment with OTULFI.
- Your doctor should watch you closely for signs and symptoms of TB while you are being treated with OTULFI.

You should not start taking OTULFI if you have any kind of infection unless your doctor says it is okay.

Before starting OTULFI, tell your doctor if you:

- think you have an infection or have symptoms of an infection such as:

  - fever, sweat, or chills
  - muscle aches
  - cough
  - shortness of breath
  - blood in phlegm

  - weight loss
  - warm, red, or painful skin or sores on your body
  - diarrhea or stomach pain
  - burning when you urinate or urinate more often than normal
  - feel very tired

- are being treated for an infection or have any open cuts.
- get a lot of infections or have infections that keep coming back.
- have TB, or have been in close contact with someone with TB.

After starting OTULFI, call your doctor right away if you have any symptoms of an infection (see above). These may be signs of infections such as chest infections, or skin infections or shingles that could have serious complications. OTULFI can make you more likely to get infections or make an infection that you have worse.
People who have a genetic problem where the body does not make any of the proteins interleukin 12 (IL-12) and interleukin 23 (IL-23) are at a higher risk for certain serious infections. These infections can spread throughout the body and cause death. People who take OTULFI may also be more likely to get these infections.
Cancers. OTULFI may decrease the activity of your immune system and increase your risk for certain types of cancers. Tell your doctor if you have ever had any type of cancer. Some people who are receiving ustekinumab products and have risk factors for skin cancer have developed certain types of skin cancers. During your treatment with OTULFI, tell your doctor if you develop any new skin growths.
Posterior Reversible Encephalopathy Syndrome (PRES). PRES is a rare condition that affects the brain and can cause death. The cause of PRES is not known. If PRES is found early and treated, most people recover. Tell your doctor right away if you have any new or worsening medical problems including:

  - headache
  - seizures

  - confusion
  - vision problems

What is OTULFI?
OTULFI is a prescription medicine used to treat:

- adults and children 6 years and older with moderate or severe psoriasis who may benefit from taking injections or pills (systemic therapy) or phototherapy (treatment using ultraviolet light alone or with pills).
- adults and children 6 years and older with active psoriatic arthritis.
- adults 18 years and older with moderately to severely active Crohn's disease.
- adults 18 years and older with moderately to severely active ulcerative colitis.

It is not known if OTULFI is safe and effective in children less than 6 years of age.

Do not take OTULFI if you are allergic to ustekinumab products or any of the ingredients in OTULFI. See the end of this Medication Guide for a complete list of ingredients in OTULFI.

Before you receive OTULFI, tell your doctor about all of your medical conditions, including if you:

- have any of the conditions or symptoms listed in the section “What is the most important information I should know about OTULFI?”
- ever had an allergic reaction to ustekinumab products. Ask your doctor if you are not sure.
- have recently received or are scheduled to receive an immunization (vaccine). People who take OTULFI should not receive live vaccines. Tell your doctor if anyone in your house needs a live vaccine. The viruses used in some types of live vaccines can spread to people with a weakened immune system and can cause serious problems. You should not receive the BCG vaccine during the one year before receiving OTULFI or one year after you stop receiving OTULFI.
- have any new or changing lesions within psoriasis areas or on normal skin.
- are receiving or have received allergy shots, especially for serious allergic reactions. Allergy shots may not work as well for you during treatment with OTULFI. OTULFI may also increase your risk of having an allergic reaction to an allergy shot.
- receive or have received phototherapy for your psoriasis.
- are pregnant or plan to become pregnant. It is not known if OTULFI can harm your unborn baby. You and your doctor should decide if you will receive OTULFI. See “What should I avoid while using OTULFI?”
- received OTULFI while you were pregnant. It is important that you tell your baby's healthcare provider before any vaccinations are given to your baby.
- are breastfeeding or plan to breastfeed. OTULFI can pass into your breast milk.
- Talk to your doctor about the best way to feed your baby if you receive OTULFI.

Tell your doctor about all the medicines you take, including prescription and over-the-counter medicines, vitamins, and herbal supplements.
Know the medicines you take. Keep a list of them to show your doctor and pharmacist when you get a new medicine.

How should I use OTULFI?

- Use OTULFI exactly as your doctor tells you to.
- Adults with Crohn's disease and ulcerative colitis will receive the first dose of OTULFI through a vein in the arm (intravenous infusion) in a healthcare facility by a healthcare provider. It takes at least 1 hour to receive the full dose of medicine. You will then receive OTULFI as an injection under the skin (subcutaneous injection) 8 weeks after the first dose of OTULFI, as described below.
- Adults with psoriasis or psoriatic arthritis, and children 6 years and older with psoriasis or psoriatic arthritis will receive OTULFI as an injection under the skin (subcutaneous injection) as described below.
- Injecting OTULFI under your skin
  - OTULFI is intended for use under the guidance and supervision of your doctor. In children 6 years and older, it is recommended that OTULFI be administered by a healthcare provider. If your doctor decides that you or a caregiver may give your injections of OTULFI at home, you should receive training on the right way to prepare and inject OTULFI. Your doctor will determine the right dose of OTULFI for you, the amount for each injection, and how often you should receive it. Do not try to inject OTULFI yourself until you or your caregiver have been shown how to inject OTULFI by your doctor or nurse.
  - Inject OTULFI under the skin (subcutaneous injection) in your upper arms, buttocks, upper legs (thighs) or stomach area (abdomen).
  - Do not give an injection in an area of the skin that is tender, bruised, red or hard.
  - Use a different injection site each time you use OTULFI.
  - If you inject more OTULFI than prescribed, call your doctor right away.
  - Be sure to keep all of your scheduled follow-up appointments.

Read the detailed Instructions for Use at the end of this Medication Guide for instructions about how to prepare and inject a dose of OTULFI, and how to properly throw away (dispose of) used needles and syringes. The syringe, needle and vial must never be re-used. After the rubber stopper is punctured,
OTULFI can become contaminated by harmful bacteria which could cause an infection if re-used. Therefore, throw away any unused portion of OTULFI.

What should I avoid while using OTULFI?
You should not receive a live vaccine while taking OTULFI. See “Before you receive OTULFI, tell your doctor about all of your medical conditions, including if you:”

What are the possible side effects of OTULFI?
OTULFI may cause serious side effects, including:

- See “What is the most important information I should know about OTULFI?”
- Serious allergic reactions. Serious allergic reactions can occur with OTULFI. Stop using OTULFI and get medical help right away if you have any of the following symptoms of a serious allergic reaction:

  - feeling faint
  - swelling of your face, eyelids, tongue, or throat

  - chest tightness
  - skin rash

- Lung inflammation. Cases of lung inflammation have happened in some people who receive ustekinumab products and may be serious. These lung problems may need to be treated in a hospital. Tell your doctor right away if you develop shortness of breath or a cough that doesn't go away during treatment with OTULFI.

Common side effects of OTULFI include:

- nasal congestion, sore throat, and runny nose
- upper respiratory infections
- fever
- headache
- tiredness
- itching
- nausea and vomiting

- redness at the injection site
- vaginal yeast infections
- urinary tract infections
- sinus infection
- bronchitis
- diarrhea
- stomach pain

These are not all of the possible side effects of OTULFI. Call your doctor for medical advice about side effects. You may report side effects to FDA at 1-800-FDA-1088.
You may also report side effects to Fresenius Kabi USA, LLC at 1-800-551-7176.

How should I store OTULFI?

- Store OTULFI vials and prefilled syringes in a refrigerator between 36°F to 46°F (2°C to 8°C).
- Store OTULFI vials standing up straight.
- Store OTULFI in the original carton to protect it from light until time to use it.
- Do not freeze OTULFI.
- Do not shake OTULFI.

If needed, individual OTULFI prefilled syringes may also be stored at room temperature up to 86°F (30°C) for a maximum single period of up to 30 days in the original carton to protect from light. Record the date when the prefilled syringe is first removed from the refrigerator on the carton in the space provided. Once a syringe has been stored at room temperature, it should not be returned to the refrigerator. Discard the syringe if not used within 30 days at room temperature storage. Do not use OTULFI after the expiration date on the carton or on the prefilled syringe.
Keep OTULFI and all medicines out of the reach of children.

General information about the safe and effective use of OTULFI.
Medicines are sometimes prescribed for purposes other than those listed in a Medication Guide. Do not use OTULFI for a condition for which it was not prescribed. Do not give OTULFI to other people, even if they have the same symptoms that you have. It may harm them. You can ask your doctor or pharmacist for information about OTULFI that was written for health professionals.

What are the ingredients in OTULFI?
Active ingredient: ustekinumab-aauz
Inactive ingredients: Single-dose prefilled syringe for subcutaneous use contains histidine, Polysorbate 80, sucrose and hydrochloric acid (to adjust pH). Single-dose vial for subcutaneous use contains histidine, Polysorbate 80, sucrose and hydrochloric acid (to adjust pH). Single-dose vial for intravenous infusion contains edetate disodium, histidine, L-histidine hydrochloride monohydrate, methionine, Polysorbate 80, and sucrose.
Manufactured by: Fresenius Kabi USA, LLC, Lake Zurich, IL 60047, U.S.A, US License Number 2146
For more information, call 1-833-522-4227 or visit the patient support program website: www.kabicare.com

This Medication Guide has been approved by the U.S. Food and Drug Administration Revised: 03/2025

INSTRUCTIONS FOR USE

OTULFI [oh tool fee]

(ustekinumab-aauz)

injection, for subcutaneous use

Instructions for injecting OTULFI using a prefilled syringe.

Read this Instructions for Use before you start using OTULFI. Your doctor or nurse should show you how to prepare and give your injection of OTULFI the right way.

If you cannot give yourself the injection:

- ask your doctor or nurse to help you, or
- ask someone who has been trained by a doctor or nurse to give your injections.

Do not try to inject OTULFI yourself until you have been shown how to inject OTULFI by your doctor, nurse or health professional.

Important information:

- Before you start, check the carton to make sure that it is the right dose. You will have either 45 mg or 90 mg as prescribed by your doctor.
  - If your dose is 45 mg, you will receive one 45 mg prefilled syringe.
  - If your dose is 90 mg, you will receive either one 90 mg prefilled syringe or two 45 mg prefilled syringes. If you receive two 45 mg prefilled syringes for a 90 mg dose, you will need to give yourself two injections, one right after the other.
- Children 12 years of age and older with psoriasis, who weigh 132 pounds (60 kg) or more may use a prefilled syringe.
- Store OTULFI in a refrigerator between 36°F to 46°F (2°C to 8°C) in the original carton to protect from light.
- If needed, individual OTULFI prefilled syringes may also be stored at room temperature up to 86°F (30°C) for a maximum single period of up to 30 days in the original carton to protect from light. Record the date when the prefilled syringe is first removed from the refrigerator on the carton in the space provided. If a syringe has been stored at room temperature, it should not be returned to the refrigerator.
- Check the expiration date on the prefilled syringe and carton. If the expiration date has passed or if the prefilled syringe has been kept at room temperature up to 86°F (30°C) for longer than a maximum single period of 30 days or if the prefilled syringe has been stored above 86°F (30°C), do not use it. If the expiration date has passed or if the prefilled syringe has been stored above 86°F (30°C), call your doctor or pharmacist, or call or call manufacturer`s phone for help.
- Make sure the syringe is not damaged.
- Check your prefilled syringe for any particles or discoloration. Your prefilled syringe should look clear and colorless to slightly brown-yellow.
- Do not use if it is frozen, discolored, cloudy or has particles. Get a new prefilled syringe.
- Do not shake the prefilled syringe at any time. Shaking your prefilled syringe may damage your OTULFI medicine. If your prefilled syringe has been shaken, do not use it. Get a new prefilled syringe.
- To reduce the risk of accidental needle sticks, each prefilled syringe has a needle guard that is automatically activated to cover the needle after you have given your injection. Do not pull back on the plunger at any time.

Gather the supplies you will need to prepare and to give your injection. (See Figure A)

You will need:

- antiseptic wipes
- cotton balls or gauze pads
- adhesive bandage
- your prescribed dose of OTULFI (See Figure B)
- FDA-cleared sharps disposal container. See "Step 4: Dispose of the syringe."

Figure A

Figure B

To prevent early activation of the needle safety guard, do not touch the NEEDLE GUARD ACTIVATION CLIPS at any time during use.

Step 1: Prepare the injection.

- Choose a well-lit, clean, flat work surface.
- Wash your hands well with soap and warm water.
- Hold the prefilled syringe with the covered needle pointing upward.

Step 2: Prepare your injection site

- Choose an injection site around your stomach area (abdomen), buttocks, upper legs (thighs). If a caregiver is giving you the injection, the outer area of the upper arms may also be used. (See Figure C)
- Use a different injection site for each injection. Do not give an injection in an area of the skin that is tender, bruised, red or hard.
- Clean the skin with an antiseptic wipe where you plan to give your injection.
- Do not touch this area again before giving the injection. Let your skin dry before injecting.
- Do not fan or blow on the clean area.

Figure C

*Areas in gray are recommended injection sites.

Step 3: Inject OTULFI

- Remove the needle cover when you are ready to inject your OTULFI.
- Do not touch the plunger or plunger head while removing the needle cover.
- Hold the body of the prefilled syringe with one hand and pull the needle cover straight off. (See Figure D)
- Put the needle cover in the trash.
- You may also see a drop of liquid at the end of the needle. This is normal.
- Do not touch the needle or let it touch anything.
- Do not use the prefilled syringe if it is dropped without the needle cover in place or if it is dropped onto a hard surface. Call your doctor, nurse or health professional for instructions.
Figure D
- Hold the body of the prefilled syringe in one hand between the thumb and index fingers. (See Figure E)

Figure E

- Do not pull back on the plunger at any time.
- Use the other hand to gently pinch the cleaned area of skin. Hold firmly.
- Use a quick, dart-like motion to insert the needle into the pinched skin at about a 45-degree angle. (See Figure F)

Figure F

- Inject all of the liquid by using your thumb to push in the plunger until the plunger head is completely between the needle guard wings. (See Figure G)

Figure G

- When the plunger is pushed as far as it will go, keep pressure on the plunger head. Take the needle out of the skin and let go of the skin.
- Slowly take your thumb off the plunger head. This will let the empty syringe move up until the entire needle is covered by the needle guard. (See Figure H)

Figure H

- When the needle is pulled out of your skin, there may be a little bleeding at the injection site. This is normal. You can press a cotton ball or gauze pad to the injection site if needed. Do not rub the injection site. You may cover the injection site with a small adhesive bandage, if necessary.

If your dose is 90 mg, you will receive either one 90 mg prefilled syringe or two 45 mg prefilled syringes. If you receive two 45 mg prefilled syringes for a 90 mg dose, you will need to give yourself a second injection right after the first. Repeat Steps 1–3 for the second injection using a new syringe. Choose a different site for the second injection.

Step 4: Dispose of the syringe.

- Put the syringe in an FDA-cleared sharps disposal container right away after use. Do not throw away (dispose of) loose syringes in your household trash.
- If you do not have an FDA-cleared sharps disposal container, you may use a household container that is:
  - made of heavy-duty plastic.
  - can be closed with a tight-fitting, puncture-resistant lid, without sharps being able to come out.
  - upright and stable during use,
  - leak-resistant,
  - and properly labeled to warn of hazardous waste inside the container.
- When your sharps disposal container is almost full, you will need to follow your community guidelines for the right way to dispose of your sharps disposal container. There may be local or state laws about how to throw away syringes and needles. For more information about safe sharps disposal, and for specific information about sharps disposal in the state that you live in, go to the FDA's website at: http://www.fda.gov/safesharpsdisposal.
- Do not dispose of your sharps disposal container in your household trash unless your community guidelines permit this. Do not recycle your sharps disposal container.
- If you have any questions, talk to your doctor or pharmacist.

Keep OTULFI and all medicines out of the reach of children.

Manufactured by:

Fresenius Kabi USA, LLC, Lake Zurich, IL 60047, U.S.A, US License Number 2146

This Instructions for Use has been approved by the U.S. Food and Drug Administration.

Issued: 09/2024

INSTRUCTIONS FOR USE

OTULFI (oh tool fee)

(ustekinumab-aauz)

injection, for subcutaneous use

lnstructions for injecting OTULFI from a vial.

Read this lnstructions for Use before you start using OTULFI. Your doctor or nurse should show you how to prepare, measure your dose, and give your injection of OTULFI the right way.

lf you cannot give yourself the injection:

- ask your doctor or nurse to help you, or
- ask someone who has been trained by a doctor or nurse to give your injections.

Do not try to inject OTULFI yourself until you have been shown how to inject OTULFI by your doctor, nurse or health professional.

lmportant information:

- Before you start, check the carton to make sure that it is the right dose. You will have either 45 mg or 90 mg as prescribed by your doctor.
  - lf your dose is 45 mg or less you will receive one 45 mg vial.
  - lf your dose is 90 mg, you will receive two 45 mg vials and you will need to give yourself two injections, one right after the other.
- Children 12 years of age and older weighing less than 132 pounds require a dose lower than 45 mg.
- Check the expiration date on the vial and carton. lf the expiration date has passed, do not use it. lf the expiration date has passed, call your doctor or pharmacist, or call Fresenius Kabi USA, LLC at 1-800-551-7176 for help.
- Check the vial for any particles or discoloration. Your vial should look clear and colorless to slightly brown-yellow.
- Do not use if it is frozen, discolored, cloudy or has particles. Get a new vial.
- Do not shake the vial at any time. Shaking your vial may damage your OTULFI medicine. lf your vial has been shaken, do not use it. Get a new vial.
- Do not use a OTULFI vial more than one time, even if there is medicine left in the vial. After the rubber stopper is punctured, OTULFI can become contaminated by harmful bacteria which could cause an infection if re-used. Therefore, throw away any unused OTULFI after you give your injection.
- Safely throw away (dispose of) OTULFI vials after use.
- Do not re-use syringes or needles. See “Step 6: Dispose of needles and syringes."
- To avoid needle-stick injuries, do not recap needles.

Storage Information

- Store OTULFI vials in a refrigerator between 36°F to 46°F (2°C to 8°C).
- Store OTULFI vials standing up straight.
- Store OTULFI in the original carton to protect it from light until time to use it.
- Do not freeze OTULFI.

Gather the supplies you will need to prepare OTULFI and to give your injection. (See Figure A)

You will need:

- a syringe with the needle attached, you will need a prescription from your healthcare provider to get syringes with the needles attached from your pharmacy.
- antiseptic wipes
- cotton balls or gauze pads
- adhesive bandage
- your prescribed dose of OTULFI
- FDA-cleared sharps disposal container. See "Step 6: Dispose of needles and syringes."

Figure A

Step 1: Prepare the injection.

- Choose a well-lit, clean, flat work surface.
- Wash your hands well with soap and warm water.

Step 2: Prepare your injection site

- Choose an injection site around your stomach area (abdomen), buttocks, and upper legs (thighs). lf a caregiver is giving you the injection, the outer area of the upper arms may also be used. (See Figure B)
- Use a different injection site for each injection. Do not give an injection in an area of the skin that is tender, bruised, red or hard.
- Clean the skin with an antiseptic wipe where you plan to give your injection.
- Do not touch this area again before giving the injection. Let your skin dry before injecting.
- Do not fan or blow on the clean area.

Figure B

*Areas in gray are recommended injection sites.

Step 3: Prepare the vial.

- Remove the cap from the top of the vial. Throw away the cap but do not remove the rubber stopper. (See Figure C)

Figure C

- Clean the rubber stopper with an antiseptic swab. (See Figure D)

Figure D

Do not touch the rubber stopper after you clean it.

- Put the vial on a flat surface.

Step 4: Prepare the needle

- Pick up the syringe with the needle attached.
- Remove the cap that covers the needle. (See Figure E)
- Throw the needle cap away. Do not touch the needle or allow the needle to touch anything.

Figure E

- Carefully pull back on the plunger to the line that matches the dose prescribed by your doctor.
- Hold the vial between your thumb and index (pointer) finger.
- Use your other hand to push the syringe needle through the center of the rubber stopper. (See Figure F)

Figure F

- Push down on the plunger until all of the air has gone from the syringe into the vial.
- Turn the vial and the syringe upside down. (See Figure G)
- Hold the OTULFI vial with one hand.
- lt is important that the needle is always in the liquid in order to prevent air bubbles forming in the syringe.
- Pull back on the syringe plunger with your other hand.
- Fill the syringe until the black tip of the plunger lines up with the mark that matches your prescribed dose.

Figure G

- Do not remove the needle from the vial. Hold the syringe with the needle pointing up to see if it has any air bubbles inside.
- lf there are air bubbles, gently tap the side of the syringe until the air bubbles rise to the top. (See Figure H)
- Slowly press the plunger up until all of the air bubbles are out of the syringe {but none of the liquid is out).
- Remove the syringe from the vial. Do not lay the syringe down or allow the needle to touch anything.

Figure H

Step 5: lnject OTULFI

- Hold the barrel of the syringe in one hand, between the thumb and index fingers.
- Do not pull back on the plunger at any time.
- Use the other hand to gently pinch the cleaned area of skin. Hold firmly.
- Use a quick, dart-like motion to insert the needle into the pinched skin at about a 45- degree angle. (See Figure I)

Figure I

- Push the plunger with your thumb as far as it will go to inject all of the liquid. Push it slowly and evenly, keeping the skin gently pinched.
- When the syringe is empty, pull the needle out of your skin and let go of the skin. (See Figure J)

Figure J

- When the needle is pulled out of your skin, there may be a little bleeding at the injection site. This is normal. You can press a cotton ball or gauze pad to the injection site if needed. Do not rub the injection site. You may cover the injection site with a small adhesive bandage, if necessary.

lf your dose is 90 mg, you will receive two 45 mg vials and you will need to give yourself a second injection right after the first. Repeat Steps 1 to 5 using a new syringe. Choose a different site for the second injection.

Step 6: Dispose of the needles and syringes.

- Do not re-use a syringe or needle.
- To avoid needle-stick injuries, do not recap a needle.
- Put your needles and syringes in an FDA-cleared sharps disposal container right away after use. Do not throw away (dispose of) loose needles and syringes in your household trash.
- lf you do not have an FDA-cleared sharps disposal container, you may use a household container that is:
  - made of heavy-duty plastic
  - can be closed with a tight-fitting, puncture-resistant lid, without sharps being able to come out
  - upright and stable during use
  - leak-resistant,
  - and properly labeled to warn of hazardous waste inside the container.
- When your sharps disposal container is almost full, you will need to follow your community guidelines for the right way to dispose of your sharps disposal container. There may be local or state laws about how to throw away syringes and needles. For more information about safe sharps disposal, and for specific information about sharps disposal in the state that you live in, go to the FDA's website at: http://www.fda.gov/safesharpsdisposal.
- Do not dispose of your sharps disposal container in your household trash unless your community guidelines permit this. Do not recycle your sharps disposal container.
- Throw away the vial into the container where you put the syringes and needles.
- lf you have any questions, talk to your doctor or pharmacist.

Keep OTULFI and all medicines out of the reach of children.

Vial Manufactured by: Fresenius Kabi USA, LLC, Lake Zurich, IL 60047, U.S.A, US License Number 2146

This Instructions for Use has been approved by the U.S. Food and Drug Administration.

Approved: 03/2025

Principal Display Panel – 45 mg Carton Label

NDC 65219-824-01

RX only

Otulfi® 45 mg/0.5 mL

ustekinumab-aauz
Injection

For subcutaneous use

1 Single-dose prefilled syringe. Discard unused portion.

Carton contains:

1 Single-dose prefilled syringe

1 Prescribing Information

1 Medication Guide

Manufactured by:

Fresenius Kabi USA, LLC

Lake Zurich, Illionis 60047

U.S. Licence No. 2146

Principal Display Panel – 45 mg Syringe Label

Single dose prefilled syringe

Discard unused portion

Otulfi®

ustekinumab-aauz
Injection

45 mg/0.5 mL

For subcutaneous use

Mfg by: Fresenius Kabi USA, LLC

U.S. License No. 2146

NDC 65219-824-01

Rx only

Store at 36 °F to 46 °F
(2 °C to 8 °C). Protect
from light. Do not shake.
Do not freeze

Principal Display Panel – 90 mg Carton Label

NDC 65219-826-26

RX only

Otulfi® 90 mg/mL

ustekinumab-aauz
Injection

For subcutaneous use

1 Single-dose prefilled syringe. Discard unused portion.

Carton contains:

1 Single-dose prefilled syringe

1 Prescribing Information

1 Medication Guide

Manufactured by:

Fresenius Kabi USA, LLC

Lake Zurich, Illionis 60047

U.S. Licence No. 2146

Principal Display Panel – 90 mg syringe Label

Single dose prefilled syringe

Discard unused portion

Otulfi®

ustekinumab-aauz
Injection

90 mg/mL

For subcutaneous use

Mfg by: Fresenius Kabi USA, LLC

U.S. License No. 2146

NDC 65219-826-26

Rx only

Store at 36 °F to 46 °F
(2 °C to 8 °C). Protect
from light. Do not shake.
Do not freeze

Principal Display Panel – 130 mg Carton Label

NDC 65219-828-05

Rx only

Otulfi®

ustekinumab-aauz
Injection

130 mg/26 mL
(5 mg/mL)

For Intravenous Infusion Only

Must be diluted

ATTENTION: Dispense
the enclosed Medication
Guide to each patient.

Carton contains:

1 Single-dose vial

1 Prescribing Information

1 Medication Guide

1 Single-dose vial.

Discard unused portion.

Principal Display Panel – 130 mg Vial Label

NDC 65219-828-05

Rx only

Otulfi®

ustekinumab-aauz
Injection

130 mg/26 mL
(5 mg/mL)

For Intravenous Infusion Only

Must be diluted

Single-dose vial.

Discard unused portion.

Dosage: See Precribing

Information

Store in a refrigerator at

36 °F (2 °C to 8 °C)

In original carton to

Protect from light

Manufactured by:

Fresenius Kabi USA, LLC

Lake Zurich,

Illinois 60047

US License No. 2146

Product of Netherlands

Principal Display Panel – 45 mg Carton Label

NDC 65219-822-05

Rx only

Otulfi®

ustekinumab-aauz
Injection

45 mg/0.5 mL

For Subcutaneous use

1 Single-dose vial.

Discard unused portion.

Manufactured by:

Fresenius Kabi USA, LLC

Lake Zurich,

Illinois 60047

U.S. License No. 2146

Principal Display Panel – 45 mg Vial Label

NDC 65219-822-05 Rx only

Otulfi®

ustekinumab-aauz

45 mg/0.5 mL

For Subcutaneous use

Single-dose vial.

Discard unused portion.

Manufactured by:

Fresenius Kabi USA, LLC

Lake Zurich,

Illinois 60047

U.S. License No. 2146